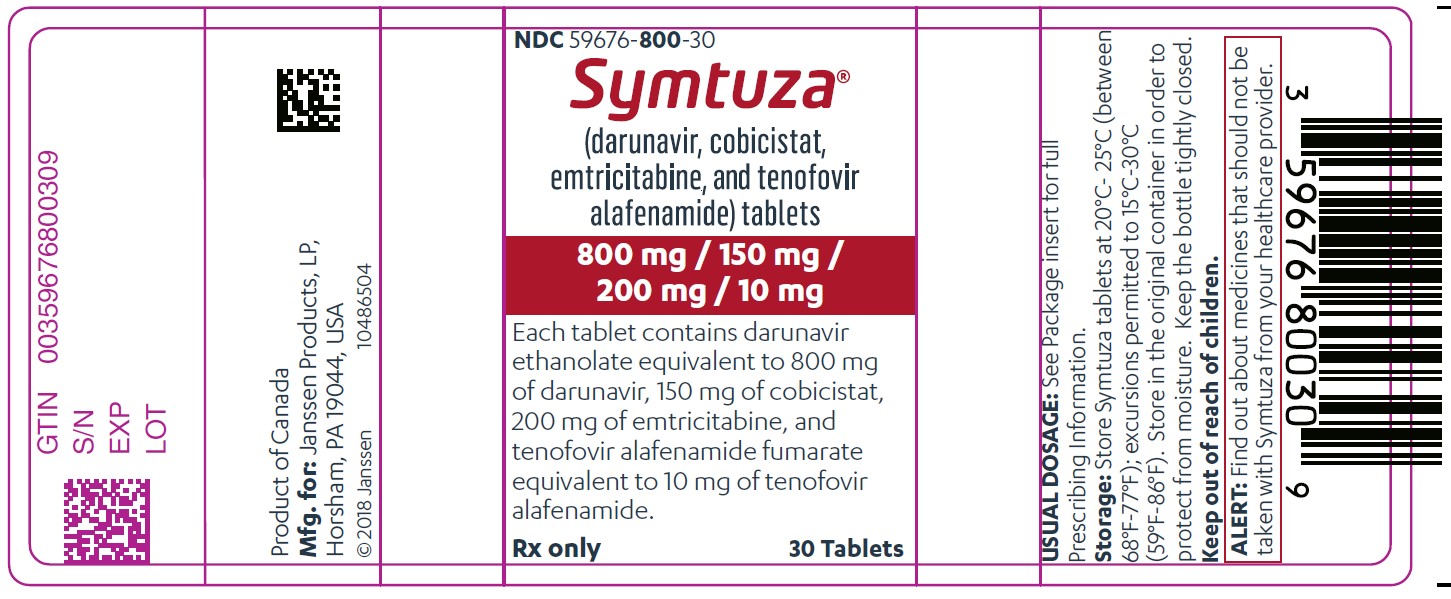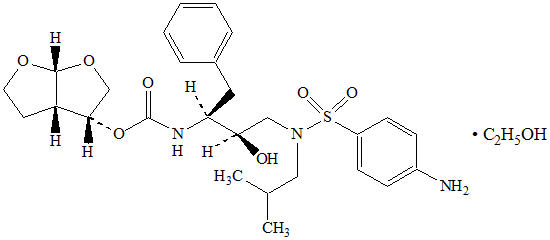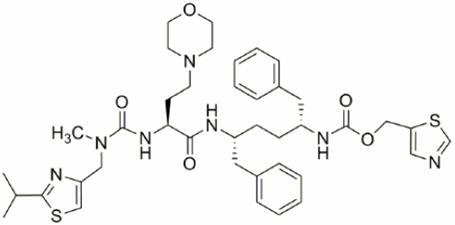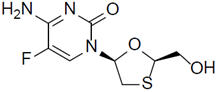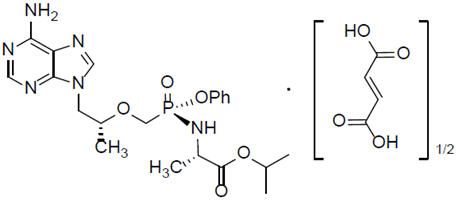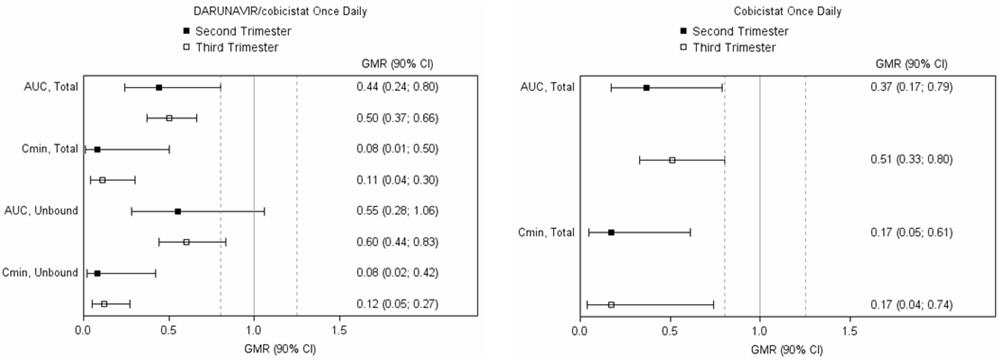 DRUG LABEL: Symtuza
NDC: 59676-800 | Form: TABLET, FILM COATED
Manufacturer: Janssen Products LP
Category: prescription | Type: HUMAN PRESCRIPTION DRUG LABEL
Date: 20240723

ACTIVE INGREDIENTS: DARUNAVIR 800 mg/1 1; COBICISTAT 150 mg/1 1; EMTRICITABINE 200 mg/1 1; TENOFOVIR ALAFENAMIDE 10 mg/1 1
INACTIVE INGREDIENTS: SILICON DIOXIDE; CROSCARMELLOSE SODIUM; MAGNESIUM STEARATE; MICROCRYSTALLINE CELLULOSE; POLYETHYLENE GLYCOL, UNSPECIFIED; TALC; TITANIUM DIOXIDE; FERRIC OXIDE YELLOW

HIGHLIGHTS OF PRESCRIBING INFORMATION

These highlights do not include all the information needed to use SYMTUZA safely and effectively. See full prescribing information for SYMTUZA.
SYMTUZA®(darunavir, cobicistat, emtricitabine, and tenofovir alafenamide) tablets, for oral use
Initial U.S. Approval: 2018

WARNING: POST TREATMENT ACUTE EXACERBATION OF HEPATITIS B

See full prescribing information for complete boxed warning.

Severe acute exacerbations of hepatitis B (HBV) have been reported in patients who are coinfected with HIV-1 and HBV and have discontinued products containing emtricitabine and/or tenofovir disoproxil fumarate (TDF), and may occur with discontinuation of SYMTUZA. Hepatic function should be monitored closely in these patients. If appropriate, anti-hepatitis B therapy may be warranted. (5.1)

RECENT MAJOR CHANGES

Contraindications (4) | 04/2022

1. INDICATIONS AND USAGE

SYMTUZA is a four-drug combination of darunavir (DRV), a human immunodeficiency virus (HIV-1) protease inhibitor, cobicistat (COBI), a CYP3A inhibitor, and emtricitabine (FTC) and tenofovir alafenamide (TAF), both HIV-1 nucleoside analog reverse transcriptase inhibitors, and is indicated as a complete regimen for the treatment of HIV-1 infection in adults and pediatric patients weighing at least 40 kg:

- who have no prior antiretroviral treatment history or
- who are virologically suppressed (HIV-1 RNA less than 50 copies per mL) on a stable antiretroviral regimen for at least 6 months and have no known substitutions associated with resistance to darunavir or tenofovir. (1)

2. DOSAGE AND ADMINISTRATION

Testing: Prior to or when initiating SYMTUZA, test patients for HBV infection.

Prior to or when initiating SYMTUZA, and during treatment with SYMTUZA, on a clinically appropriate schedule, assess serum creatinine, estimated creatinine clearance, urine glucose, and urine protein in all patients. In patients with chronic kidney disease, also assess serum phosphorus. (2.1)

Recommended dosage: One tablet taken once daily with food in adults and pediatric patients, weighing at least 40 kg. (2.2)

Renal Impairment:SYMTUZA is not recommended in patients with estimated creatinine clearance below 30 mL/min. (2.3)

Hepatic Impairment: SYMTUZA is not recommended in patients with severe hepatic impairment. (2.4)

3. DOSAGE FORMS AND STRENGTHS

Tablets: 800 mg of darunavir, 150 mg of cobicistat, 200 mg of emtricitabine, and 10 mg of tenofovir alafenamide (equivalent to 11.2 mg of tenofovir alafenamide fumarate). (3)

4. CONTRAINDICATIONS

SYMTUZA is contraindicated to be co-administered with certain drugs for which altered plasma concentrations are associated with serious and/or life-threatening events or which may lead to loss of therapeutic effect of SYMTUZA and development of resistance. (4)

5. WARNINGS AND PRECAUTIONS

- Drug-induced hepatitis (e.g., acute hepatitis, cytolytic hepatitis) including some fatalities can occur with SYMTUZA. Monitor liver function before and during therapy, especially in patients with underlying chronic hepatitis, cirrhosis, or in patients who have pre-treatment elevations of transaminases. (5.2)
- Severe skin reactions, including Stevens-Johnson syndrome, toxic epidermal necrolysis, drug rash with eosinophilia and systemic symptoms, and acute generalized exanthematous pustulosis may occur with SYMTUZA. Discontinue treatment if severe skin reaction develops. (5.3)
- Patients receiving SYMTUZA may develop new onset or exacerbations of immune reconstitution syndrome. (5.5)
- Monitor in patients with a known sulfonamide allergy. (5.7)
- Discontinue treatment in patients who develop symptoms or laboratory findings suggestive of lactic acidosis or pronounced hepatotoxicity. (5.8)
- Patients receiving SYMTUZA may develop new onset or exacerbation of diabetes mellitus/hyperglycemia and redistribution/accumulation of body fat. (5.9, 5.10)
- Patients with hemophilia may develop increase bleeding events. (5.11)

6. ADVERSE REACTIONS

The most common adverse reactions (all grades, incidence greater than or equal to 2%) were diarrhea, rash, nausea, fatigue, headache, abdominal discomfort, and flatulence. (6.1)

To report SUSPECTED ADVERSE REACTIONS, contact Janssen Products, LP at 1-800-JANSSEN (1-800-526-7736) or FDA at 1-800-FDA-1088 or www.fda.gov/medwatch.

7. DRUG INTERACTIONS

Co-administration of SYMTUZA with other drugs can alter the concentration of other drugs and other drugs may alter the concentrations of SYMTUZA components. Consult the full prescribing information prior to and during treatment for potential drug interactions. (4, 5.4, 7, 12.3)

8. USE IN SPECIFIC POPULATIONS

- Pregnancy: SYMTUZA is not recommended during pregnancy due to substantially lower exposures of darunavir and cobicistat during pregnancy. (2.5, 8.1, 12.3)
- Lactation: Breastfeeding is not recommended. (8.2)
- Pediatrics: Not recommended for pediatric patients weighing less than 40 kg (8.4)

FULL PRESCRIBING INFORMATION

WARNING: POST TREATMENT ACUTE EXACERBATION OF HEPATITIS B

Severe acute exacerbations of hepatitis B (HBV) have been reported in patients who are coinfected with HIV-1 and HBV and have discontinued products containing emtricitabine and/or tenofovir disoproxil fumarate (TDF), and may occur with discontinuation of SYMTUZA. Closely monitor hepatic function with both clinical and laboratory follow-up for at least several months in patients who are coinfected with HIV-1 and HBV and discontinue SYMTUZA. If appropriate, anti-hepatitis B therapy may be warranted [see Warnings and Precautions (5.1)] .

1. INDICATIONS AND USAGE

SYMTUZA is indicated as a complete regimen for the treatment of human immunodeficiency virus type 1 (HIV-1) infection in adults and pediatric patients weighing at least 40 kg:

- who have no prior antiretroviral treatment history or
- who are virologically suppressed (HIV-1 RNA less than 50 copies per mL) on a stable antiretroviral regimen for at least 6 months and have no known substitutions associated with resistance to darunavir or tenofovir.

2. DOSAGE AND ADMINISTRATION

2.1 Testing Prior to Initiation of SYMTUZA

Prior to or when initiating SYMTUZA, test patients for hepatitis B (HBV) virus infection [see Warnings and Precautions (5.1)] .

Prior to or when initiating SYMTUZA, and during treatment with SYMTUZA, on a clinically appropriate schedule, assess serum creatinine, estimated creatinine clearance, urine glucose, and urine protein in all patients. In patients with chronic kidney disease, also assess serum phosphorus [see Warnings and Precautions (5.6)] .

2.2 Recommended Dosage

SYMTUZA is a four-drug fixed-dose combination product containing 800 mg of darunavir (DRV), 150 mg of cobicistat (COBI), 200 mg of emtricitabine (FTC), and 10 mg of tenofovir alafenamide (TAF). The recommended dosage of SYMTUZA is one tablet taken orally once daily with food in adults and pediatric patients weighing at least 40 kg. For patients who are unable to swallow the whole tablet, SYMTUZA may be split into two pieces using a tablet-cutter, and the entire dose should be consumed immediately after splitting [see Clinical Pharmacology (12.3)] .

2.3 Not Recommended in Patients with Severe Renal Impairment

SYMTUZA is not recommended in patients with creatinine clearance below 30 mL per minute [see Use in Specific Populations (8.6)] .

2.4 Not Recommended in Patients with Severe Hepatic Impairment

SYMTUZA is not recommended for use in patients with severe hepatic impairment (Child-Pugh Class C) [see Use in Specific Populations (8.7)] .

2.5 Not Recommended During Pregnancy

SYMTUZA is not recommended during pregnancy because of substantially lower exposures of darunavir and cobicistat during the second and third trimesters [see Use in Specific Populations (8.1)and Clinical Pharmacology (12.3)].

SYMTUZA should not be initiated in pregnant individuals. An alternative regimen is recommended for those who become pregnant during therapy with SYMTUZA.

3. DOSAGE FORMS AND STRENGTHS

Each SYMTUZA tablet contains darunavir ethanolate equivalent to 800 mg of darunavir, 150 mg of cobicistat, 200 mg of emtricitabine (FTC), and tenofovir alafenamide fumarate equivalent to 10 mg of tenofovir alafenamide (TAF). The yellow to yellowish-brown, capsule-shaped, film-coated tablet is debossed with "8121" on one side and "JG" on the other side.

4. CONTRAINDICATIONS

Darunavir and cobicistat are both inhibitors of the cytochrome P450 3A (CYP3A) isoform. SYMTUZA should not be co-administered with medicinal products that are highly dependent on CYP3A for clearance and for which increased plasma concentrations are associated with serious and/or life-threatening events (narrow therapeutic index). Darunavir and cobicistat are both substrates of the cytochrome P450 3A (CYP3A) isoform. Co-administration of SYMTUZA with CYP3A inducers is expected to lower plasma concentrations of darunavir and cobicistat which may lead to loss of efficacy of darunavir and development of resistance. Examples of drugs that are contraindicated for co-administration with SYMTUZA due to the potential for serious and/or life-threatening events or loss of therapeutic effect [see Drug Interactions (7.5)] are listed below.

- Alpha 1-adrenoreceptor antagonist: alfuzosin
- Anticonvulsants: carbamazepine, phenobarbital, phenytoin
- Anti-gout: colchicine, in patients with renal and/or hepatic impairment
- Antimycobacterial: rifampin
- Antipsychotics: lurasidone, pimozide
- Cardiac Disorders: dronedarone, ivabradine, ranolazine
- Ergot derivatives, e.g., dihydroergotamine, ergotamine, methylergonovine
- Herbal product: St. John's wort (Hypericum perforatum)
- Hepatitis C direct acting antiviral: elbasvir/grazoprevir
- Lipid modifying agents: lomitapide, lovastatin, simvastatin
- Opioid Antagonist: naloxegol
- PDE-5 inhibitor: sildenafil when used for treatment of pulmonary arterial hypertension
- Sedatives/hypnotics: orally administered midazolam, triazolam

5. WARNINGS AND PRECAUTIONS

5.1 Severe Acute Exacerbation of Hepatitis B in Patients Coinfected with HIV-1 and HBV

Patients with HIV-1 should be tested for the presence of chronic hepatitis B virus before initiating antiretroviral therapy [see Dosage and Administration (2.1)] . Severe acute exacerbations of hepatitis B (e.g., liver decompensation and liver failure) have been reported in patients who are coinfected with HIV-1 and HBV and have discontinued products containing emtricitabine and/or tenofovir disoproxil fumarate, and may occur with discontinuation of SYMTUZA. Patients coinfected with HIV-1 and HBV who discontinue SYMTUZA should be closely monitored with both clinical and laboratory follow-up for at least several months after stopping treatment. If appropriate, anti-hepatitis B therapy may be warranted, especially in patients with advanced liver disease or cirrhosis, since post-treatment exacerbation of hepatitis may lead to hepatic decompensation and liver failure.

5.2 Hepatotoxicity

Drug-induced hepatitis (e.g., acute hepatitis, cytolytic hepatitis) has been reported in clinical trials with darunavir, a component of SYMTUZA. Patients with pre-existing liver dysfunction, including chronic active hepatitis B or C, have an increased risk for liver function abnormalities including severe hepatic adverse reactions.

Post-marketing cases of liver injury, including some fatalities, have been reported with darunavir. These have generally occurred in patients with advanced HIV-1 disease taking multiple concomitant medications, having co-morbidities including hepatitis B or C co-infection, and/or developing immune reconstitution syndrome. A causal relationship with darunavir therapy has not been established.

Appropriate laboratory testing should be conducted prior to initiating therapy with SYMTUZA and patients should be monitored during treatment as clinically appropriate. Increased AST/ALT monitoring should be considered in patients with underlying chronic hepatitis, cirrhosis, or in patients who have pre-treatment elevations of transaminases, especially during the first several months of SYMTUZA treatment.

Evidence of new or worsening liver dysfunction (including clinically significant elevation of liver enzymes and/or symptoms such as fatigue, anorexia, nausea, jaundice, dark urine, liver tenderness, hepatomegaly) should prompt consideration of interruption or discontinuation of SYMTUZA.

5.3 Severe Skin Reactions

In patients receiving darunavir, a component of SYMTUZA, severe skin reactions may occur. These include conditions accompanied by fever and/or elevations of transaminases. Stevens-Johnson syndrome was reported with darunavir co-administered with cobicistat in clinical trials at a rate of 0.1%. During darunavir post-marketing experience, toxic epidermal necrolysis, drug rash with eosinophilia and systemic symptoms (DRESS), and acute generalized exanthematous pustulosis have been reported. Discontinue SYMTUZA immediately if signs or symptoms of severe skin reactions develop. These can include but are not limited to severe rash or rash accompanied with fever, general malaise, fatigue, muscle or joint aches, blisters, oral lesions, conjunctivitis, hepatitis, and/or eosinophilia.

Rash events of any cause and any grade occurred in 15% of subjects with no prior antiretroviral treatment history treated with SYMTUZA in the AMBER trial [see Adverse Reactions (6.1)] . Rash events were mild-to-moderate, often occurring within the first four weeks of treatment and resolving with continued dosing. The discontinuation rate due to rash in subjects using SYMTUZA was 2%.

5.4 Risk of Serious Adverse Reactions or Loss of Virologic Response Due to Drug Interactions

The concomitant use of SYMTUZA and other drugs may result in known or potentially significant drug interactions which may lead to [see Contraindications (4)and Drug Interactions (7.5)] :

- Clinically significant adverse reactions from greater exposures of concomitant drugs.
- Clinically significant adverse reactions from greater exposures of SYMTUZA.
- Loss of therapeutic effect of the concomitant drugs from lower exposures of active metabolite(s).
- Loss of therapeutic effect of SYMTUZA and possible development of resistance from lower exposures of SYMTUZA.

See Table 4for steps to prevent or manage these possible and known significant drug interactions, including dosing recommendations. Consider the potential for drug interactions prior to and during SYMTUZA therapy; review concomitant medications during SYMTUZA therapy; and monitor for the adverse reactions associated with concomitant medications [see Contraindications (4)and Drug Interactions (7)] .

When used with concomitant medications, SYMTUZA, which contains darunavir boosted with cobicistat, may result in different drug interactions than those observed or expected with darunavir co-administered with ritonavir. Complex or unknown mechanisms of drug interactions preclude extrapolation of drug interactions with darunavir co-administered with ritonavir to certain SYMTUZA interactions [see Drug Interactions (7)and Clinical Pharmacology (12.3)] .

5.5 Immune Reconstitution Syndrome

Immune reconstitution syndrome has been reported in patients treated with combination antiretroviral therapy. During the initial phase of combination antiretroviral treatment, patients whose immune systems respond may develop an inflammatory response to indolent or residual opportunistic infections (such as Mycobacterium aviuminfection, cytomegalovirus, Pneumocystis jiroveciipneumonia [PCP], or tuberculosis), which may necessitate further evaluation and treatment.

Autoimmune disorders (such as Graves' disease, polymyositis, Guillain-Barré syndrome, and autoimmune hepatitis) have also been reported to occur in the setting of immune reconstitution; however, the time to onset is more variable, and can occur many months after initiation of antiretroviral treatment.

5.6 New Onset or Worsening Renal Impairment

Postmarketing cases of renal impairment, including acute renal failure, proximal renal tubulopathy (PRT), and Fanconi syndrome have been reported with TAF-containing products; while most of these cases were characterized by potential confounders that may have contributed to the reported renal events, it is also possible these factors may have predisposed patients to tenofovir-related adverse events [see Adverse Reactions (6.1, 6.2)] . SYMTUZA is not recommended in patients with estimated creatinine clearance below 30 mL per minute.

Patients taking tenofovir prodrugs who have impaired renal function and those taking nephrotoxic agents including non-steroidal anti-inflammatory drugs are at increased risk of developing renal-related adverse reactions.

Prior to or when initiating SYMTUZA and during treatment with SYMTUZA, on a clinically appropriate schedule, assess serum creatinine, estimated creatinine clearance, urine glucose, and urine protein in all patients. In patients with chronic kidney disease, also assess serum phosphorus. Discontinue SYMTUZA in patients who develop clinically significant decreases in renal function or evidence of Fanconi syndrome.

Cobicistat, a component of SYMTUZA, produces elevations of serum creatinine due to inhibition of tubular secretion of creatinine without affecting glomerular filtration. This effect should be considered when interpreting changes in estimated creatinine clearance in patients initiating SYMTUZA, particularly in patients with medical conditions or receiving drugs needing monitoring with estimated creatinine clearance. The elevation is typically seen within 2 weeks of starting therapy and is reversible after discontinuation. Patients who experience a confirmed increase in serum creatinine of greater than 0.4 mg/dL should be closely monitored for renal safety.

5.7 Sulfa Allergy

Darunavir contains a sulfonamide moiety. Monitor patients with a known sulfonamide allergy after initiating SYMTUZA. In clinical studies with darunavir co-administered with ritonavir, the incidence and severity of rash were similar in subjects with or without a history of sulfonamide allergy.

5.8 Lactic Acidosis/Severe Hepatomegaly with Steatosis

Lactic acidosis and severe hepatomegaly with steatosis, including fatal cases, have been reported with the use of nucleoside analogs, including emtricitabine, a component of SYMTUZA, and TDF, another prodrug of tenofovir, alone or in combination with other antiretrovirals. Treatment with SYMTUZA should be suspended in any patient who develops clinical or laboratory findings suggestive of lactic acidosis or pronounced hepatotoxicity (which may include hepatomegaly and steatosis even in the absence of marked transaminase elevations).

5.9 Diabetes Mellitus/Hyperglycemia

New onset diabetes mellitus, exacerbation of pre-existing diabetes mellitus, and hyperglycemia have been reported during postmarketing surveillance in HIV infected patients receiving HIV protease inhibitor (PI) therapy. Some patients required either initiation or dose adjustments of insulin or oral hypoglycemic agents for treatment of these events. In some cases, diabetic ketoacidosis has occurred. In those patients who discontinued PI therapy, hyperglycemia persisted in some cases. Because these events have been reported voluntarily during clinical practice, estimates of frequency cannot be made and causal relationships between HIV PI therapy and these events have not been established.

5.10 Fat Redistribution

Redistribution/accumulation of body fat, including central obesity, dorsocervical fat enlargement (buffalo hump), peripheral wasting, facial wasting, breast enlargement, and "cushingoid appearance" have been observed in patients receiving antiretroviral therapy. The mechanism and long-term consequences of these events are currently unknown. A causal relationship has not been established.

5.11 Hemophilia

There have been reports of increased bleeding, including spontaneous skin hematomas and hemarthrosis in patients with hemophilia type A and B treated with HIV protease inhibitors (PIs). In some patients, additional factor VIII was given. In more than half of the reported cases, treatment with HIV PIs was continued or reintroduced if treatment had been discontinued. A causal relationship between PI therapy and these episodes has not been established.

6. ADVERSE REACTIONS

The following adverse reactions are discussed in other sections of the labeling:

- Severe acute exacerbations of hepatitis B [see Warnings and Precautions (5.1)]
- Hepatotoxicity [see Warnings and Precautions (5.2)]
- Severe skin reactions [see Warnings and Precautions (5.3)]
- Immune reconstitution syndrome [see Warnings and Precautions (5.5)]
- New onset or worsening renal impairment [see Warnings and Precautions (5.6)]
- Lactic acidosis/severe hepatomegaly with steatosis [see Warnings and Precautions (5.8)]

6.1 Clinical Trials Experience

Because clinical trials are conducted under widely varying conditions, adverse reaction rates observed in the clinical trials of a drug cannot be directly compared to rates in the clinical trials of another drug and may not reflect the rates observed in practice.

Clinical Trials in Adults

Adverse Reactions in Adults with No Prior Antiretroviral Treatment History

The safety profile of SYMTUZA in HIV-1 infected adults with no prior antiretroviral treatment history is based on Week 48 data from the AMBER trial, a randomized, double-blind, active-controlled trial where a total of 362 subjects received SYMTUZA once daily and 363 subjects received a combination of PREZCOBIX®(fixed-dose combination of darunavir and cobicistat) and fixed-dose combination of emtricitabine and tenofovir disoproxil fumarate (FTC/TDF).

The proportion of subjects who discontinued treatment with SYMTUZA or PREZCOBIX+FTC/TDF due to adverse events, regardless of severity, were 2% and 4% respectively.

An overview of the most frequent (occurring in at least 2% of subjects) adverse reactions irrespective of severity reported in AMBER are presented in Table 1. An overview of the most frequent laboratory abnormalities of at least Grade 2 severity reported in AMBER are presented in Table 2. Changes from baseline in lipid parameters for patients receiving SYMTUZA and those receiving PREZCOBIX + FTC/TDF are presented in Table 3.

Most adverse reactions during treatment with SYMTUZA were grade 1 or 2 in severity. One grade 3 adverse reaction was reported and no grade 4 adverse reactions were reported during treatment with SYMTUZA.

Table 1: Adverse Reactions Reported in ≥2% of HIV-1 Infected Adults With No Prior Antiretroviral Treatment History in AMBER (Week 48 Analysis)
 | SYMTUZA (N=362) |  | PREZCOBIX+FTC/TDF (N=363)
 | All Grades | At least Grade 2 | All Grades | At least Grade 2
Diarrhea | 9% | 2% | 11% | 2%
Rash [Includes pooled reported terms: dermatitis, dermatitis allergic, erythema, photosensitivity reaction, rash, rash generalized, rash macular, rash maculo-papular, rash morbilliform, rash pruritic, toxic skin eruption, urticaria] | 8% | 4% | 7% | 5%
Nausea | 6% | 1% | 10% | 3%
Fatigue | 4% | 1% | 4% | 1%
Headache | 3% | 1% | 2% | 1%
Abdominal discomfort | 2% | - | 4% | <1%
Flatulence | 2% | <1% | 1% | -

Adverse Reactions in Virologically-Suppressed Adults

The safety profile of SYMTUZA in virologically-suppressed HIV-1 infected adults is based on Week 48 data from 1,141 subjects in the EMERALD trial, a randomized, open-label, active-controlled trial where 763 subjects with a stable antiretroviral regimen consisting of a boosted protease inhibitor (bPI) [either darunavir once daily or atazanavir (both boosted with ritonavir or cobicistat), or lopinavir with ritonavir] combined with FTC/TDF switched to SYMTUZA, and 378 subjects who continued their treatment regimen of a bPI with FTC/TDF. Overall, the safety profile of SYMTUZA in subjects in this study was similar to that in subjects with no prior antiretroviral treatment history. The proportion of subjects who discontinued treatment with SYMTUZA due to adverse events, regardless of severity, was 1%.

Less Frequent Adverse Reactions

The following adverse reactions occurred in less than 2% of adults with no antiretroviral treatment history or virologically suppressed subjects receiving SYMTUZA, or are from studies described in the prescribing information of the individual component PREZISTA (darunavir).

Gastrointestinal Disorders: dyspepsia, pancreatitis (acute), vomiting

Skin and Subcutaneous Tissue Disorders: angioedema, pruritus, Stevens-Johnson syndrome

Metabolism and Nutrition Disorders: anorexia, diabetes mellitus, lipodystrophy

Reproductive System and Breast Disorders: gynecomastia

Musculoskeletal and Connective Tissue Disorders: myalgia, osteonecrosis

Psychiatric Disorders: abnormal dreams

Immune System Disorders: (drug) hypersensitivity, immune reconstitution inflammatory syndrome

Hepatobiliary Disorders: acute hepatitis

Laboratory Abnormalities

Table 2: Laboratory Abnormalities (Grade 2–4) Reported in ≥2% of Adults With No Prior Antiretroviral Treatment History in AMBER (Week 48 Analysis)
Laboratory Parameter Grade | Limit | SYMTUZA N=362 | PREZCOBIX+FTC/TDF N=363
Creatinine
Grade 2 | >1.3 to 1.8 × ULN | 4% | 14%
Grade 4 | ≥3.5× ULN | <1% | 0
Triglycerides
Grade 2 | 301–500 mg/dL | 7% | 4%
Grade 3 | 501–1,000 mg/dL | 1% | 1%
Grade 4 | >1,000 mg/dL | <1% | <1%
Total Cholesterol
Grade 2 | 240–<300 mg/dL | 17% | 4%
Grade 3 | ≥ 300 mg/dL | 2% | 1%
Low-Density Lipoprotein Cholesterol
Grade 2 | 160–189 mg/dL | 9% | 4%
Grade 3 | ≥190 mg/dL | 5% | 1%
Elevated Glucose Levels
Grade 2 | 126–250 mg/dL | 6% | 6%
Grade 3 | 251–500 mg/dL | <1% | 0

ALT and/or AST elevations (Grade 2–4 combined) occurred in 2% of adult subjects receiving SYMTUZA with no antiretroviral treatment history in AMBER (Week 48 Analysis). Results were consistent in subjects receiving PREZCOBIX+FTC/TDF.

Table 3: Lipid Values, Mean Change from Baseline, Reported in Adults With No Prior Antiretroviral Treatment History in AMBER (Week 48 Analysis)
 | SYMTUZA N=362 |  | PREZCOBIX+FTC/TDF N=363
 | Baseline | Week 48 | Baseline | Week 48
Mean [The change from baseline is the mean of within-subject changes from baseline for subjects with both baseline and Week 48 values, or the last value carried forward prior to initiating lipid-lowering agent post-baseline.] | mg/dL | Change | mg/dL | Change
N [N corresponds to the number of subjects with paired values and not on a lipid-lowering agent at screening/baseline. Subjects on lipid-lowering agents at screening/baseline were excluded from the analysis (6 out of 362 subjects on SYMTUZA, 8 out of 363 subjects on PREZCOBIX+FTC/TDF). Subjects initiating a lipid-lowering agent post-baseline had their last fasted on-treatment value (prior to starting the agent) carried forward (6 on SYMTUZA, 2 on PREZCOBIX+FTC/TDF).] | N=304 [One subject did not have a Week 48 result for LDL cholesterol (n=303).] |  | N=290
Total cholesterol | 168 | +30 | 164 | +11
HDL cholesterol | 45 | +6 | 44 | +2
LDL cholesterol | 100 | +19 | 98 | +5
Triglycerides | 117 | +34 | 112 | +21
Total cholesterol to HDL ratio | 4.1 | 0.2 | 4.0 | 0.1

The percentage of subjects starting any lipid lowering drug during treatment in the SYMTUZA and PREZCOBIX + FTC/TDF arm were 1.7% (n=6) and 0.6% (n=2), respectively.

Renal Laboratory Tests

In the AMBER trial, which enrolled 725 adults with no prior antiretroviral treatment history, subjects had a median baseline eGFR (estimated glomerular filtration rate) of 119 mL/min (SYMTUZA) and 118 mL/min (PREZCOBIX + FTC/TDF). From baseline to Week 48, mean (SD) serum creatinine increased by 0.05 (0.10) mg/dL in the SYMTUZA group and by 0.09 (0.11) mg/dL in the PREZCOBIX + FTC/TDF group. Median serum creatinine was 0.90 mg/dL (SYMTUZA) and 0.89 mg/dL (PREZCOBIX + FTC/TDF) at baseline and 0.95 mg/dL (SYMTUZA) and 0.97 mg/dL (PREZCOBIX +FTC/TDF) at Week 48. Increases in serum creatinine occurred by Week 2 of treatment and remained stable. Median urine protein-to-creatinine ratio (UPCR) was 47 mg/g (SYMTUZA) and 51 mg/g (PREZCOBIX + FTC/TDF) at baseline and 30 mg/g (SYMTUZA) and 34 mg/g (PREZCOBIX + FTC/TDF) at Week 48.

In the EMERALD trial which had 1,141 virologically-suppressed adults treated with an HIV protease inhibitor and TDF containing regimen with a median baseline eGFR of 104 mL/min (SYMTUZA) and 103 mL/min (bPI+FTC/TDF) who were randomized to continue their treatment regimen or switch to SYMTUZA, at Week 48, mean serum creatinine was similar to baseline for both those continuing baseline treatment and those switching to SYMTUZA. Mean (SD) serum creatinine was 0.98 (0.18) mg/dL (SYMTUZA) and 0.98 (0.19) mg/dL (bPI+FTC/TDF) at baseline and 0.99 (0.18) mg/dL (SYMTUZA) and 0.99 (0.21) mg/dL (bPI+FTC/TDF) at Week 48. Median serum creatinine was 0.97 mg/dL (SYMTUZA) and 0.98 mg/dL (bPI+FTC/TDF) at baseline and 1.0 mg/dL (SYMTUZA) and 0.97 mg/dL (bPI+FTC/TDF) at Week 48. Median UPCR was 62 mg/g (SYMTUZA) and 63 mg/g (bPI+FTC/TDF) at baseline and 37 mg/g (SYMTUZA) and 53 mg/g (bPI+FTC/TDF) at Week 48.

Bone Mineral Density

AMBER

The effects of SYMTUZA compared to PREZCOBIX + FTC/TDF on bone mineral density (BMD) change from baseline to Week 48 were assessed by dual-energy X-ray absorptiometry (DXA). The mean percentage change in BMD from baseline to Week 48 was −0.7% with SYMTUZA compared to −2.4% with PREZCOBIX + FTC/TDF at the lumbar spine and 0.2% compared to −2.7% at the total hip. BMD declines of 5% or greater at the lumbar spine were experienced by 16% of SYMTUZA subjects and 22% of PREZCOBIX + FTC/TDF subjects. BMD declines of 7% or greater at the femoral neck were experienced by 2% of SYMTUZA subjects and 15% of PREZCOBIX + FTC/TDF subjects. The long-term clinical significance of these BMD changes is not known.

EMERALD

In EMERALD, bPI and TDF-treated subjects were randomized to continue their TDF-based regimen or switch to SYMTUZA; changes in BMD from baseline to Week 48 were assessed by DXA. The mean percentage change in BMD from baseline to Week 48 was 1.5% with SYMTUZA compared to −0.6% with bPI + FTC/TDF at the lumbar spine and 1.4% compared to -0.3% at the total hip. BMD declines of 5% or greater at the lumbar spine were experienced by 2% of SYMTUZA subjects and 9% of bPI + FTC/TDF subjects. BMD declines of 7% or greater at the femoral neck were experienced by no SYMTUZA subjects and 2% of bPI + FTC/TDF subjects. The long-term clinical significance of these BMD changes is not known.

Clinical Trials in Pediatric Patients

Adverse Reactions in Pediatric Patients Weighing At Least 40 kg

No clinical trials with SYMTUZA were performed in pediatric patients. However, the safety of the components of SYMTUZA was evaluated in pediatric subjects of 12 to less than 18 years of age through clinical trials GS-US-216-0128 (virologically-suppressed, N=7 with weight ≥40 kg) for darunavir co-administered with cobicistat and other antiretroviral agents, and GS-US-292-0106 (treatment-naïve, N=50 with weight ≥35 kg) for a fixed-dose combination regimen containing cobicistat, emtricitabine, and tenofovir alafenamide together with elvitegravir. Safety analyses of the trials in these pediatric subjects did not identify new safety concerns compared to the known safety profile of SYMTUZA in adult subjects [see Clinical Studies (14.3)] .

6.2 Postmarketing Experience

The following adverse reactions have been identified during post-approval use of darunavir. Because these reactions are reported voluntarily from a population of uncertain size, it is not always possible to reliably estimate their frequency or establish a causal relationship to drug exposure.

Metabolism and Nutrition Disorders:

Redistribution of body fat

Musculoskeletal and Connective Tissue Disorders:

Rhabdomyolysis (associated with co-administration with HMG-CoA reductase inhibitors)

Skin and Subcutaneous Tissue Disorders:

Toxic epidermal necrolysis, acute generalized exanthematous pustulosis, drug rash with eosinophilia and systemic symptoms [see Warnings and Precautions (5.3)]

Renal and Urinary Disorders:

Acute renal failure, acute tubular necrosis, proximal renal tubulopathy, Fanconi syndrome [see Warnings and Precautions (5.6)] , crystal nephropathy, and crystalluria

7. DRUG INTERACTIONS

7.1 Not Recommended With Other Antiretroviral Medications

SYMTUZA is a complete regimen for HIV-1 infection and co-administration with other antiretroviral medications for the treatment of HIV-1 infection is not recommended. For this reason, information regarding potential drug-drug interactions with other antiretroviral medications is not provided.

7.2 Potential for SYMTUZA to Affect Other Drugs

Darunavir co-administered with cobicistat is an inhibitor of CYP3A and CYP2D6. Cobicistat inhibits the following transporters: P-glycoprotein (P-gp), BCRP, MATE1, OATP1B1 and OATP1B3. Therefore, co-administration of SYMTUZA with drugs that are primarily metabolized by CYP3A and/or CYP2D6, or are substrates of P-gp, BCRP, MATE1, OATP1B1 or OATP1B3 may result in increased plasma concentrations of such drugs, which could increase or prolong their therapeutic effect and can be associated with adverse events. Co-administration of SYMTUZA with drugs that have active metabolite(s) formed by CYP3A may result in reduced plasma concentrations of these active metabolite(s), potentially leading to loss of their therapeutic effect (see Table 4).

7.3 Potential for Other Drugs to Affect SYMTUZA

Darunavir is metabolized by CYP3A. Cobicistat is metabolized by CYP3A and, to a minor extent, by CYP2D6. Co-administration of drugs that induce CYP3A activity are expected to increase the clearance of darunavir and cobicistat, resulting in lowered plasma concentrations which may lead to loss of therapeutic effect and development of resistance. Co-administration of SYMTUZA with other drugs that inhibit CYP3A may result in increased plasma concentrations of darunavir and cobicistat (see Table 4).

Tenofovir alafenamide (TAF) is a substrate of P-gp, BCRP, OATP1B1, and OATP1B3. Drugs that strongly affect P-gp activity may lead to changes in TAF absorption. Drugs that induce P-gp activity are expected to decrease the absorption of TAF, resulting in decreased plasma concentrations of TAF, which may lead to loss of therapeutic effect of SYMTUZA and development of resistance. Co-administration of SYMTUZA with other drugs that inhibit P-gp may increase the absorption and plasma concentrations of TAF (see Table 4).

7.4 Drugs Affecting Renal Function

Because emtricitabine and tenofovir are primarily excreted by the kidneys through glomerular filtration and active tubular secretion, co-administration of SYMTUZA with drugs that reduce renal function or compete for active tubular secretion may increase concentrations of emtricitabine, tenofovir, and other renally eliminated drugs and this may increase the risk of adverse reactions. Some examples of drugs that are eliminated by active tubular secretion include, but are not limited to, acyclovir, cidofovir, ganciclovir, valacyclovir, valganciclovir, aminoglycosides (e.g., gentamicin), and high-dose or multiple NSAIDs [see Warnings and Precautions (5.6)] .

7.5 Significant Drug Interactions

Table 4 provides examples of established or potentially clinically significant drug interactions with SYMTUZA and recommended steps to prevent or manage these interactions. These recommendations are based on drug interaction trials conducted with the components of SYMTUZA, as individual agents or in combination, or are predicted interactions. No drug interaction trials have been performed with SYMTUZA or with all the components administered together. Drug interaction trials have been conducted with darunavir co-administered with ritonavir or cobicistat or with emtricitabine and tenofovir prodrugs. The table includes potentially significant interactions but is not all inclusive ,and therefore the label of each drug that is co- administered with SYMTUZA should be consulted for information related to the route of metabolism, interaction pathways, potential risks, and specific actions to be taken with regard to co- administration.

Table 4: Significant Drug Interactions
Concomitant Drug Class: Drug Name Examples | Effect on Concentration | Clinical Comment
Alpha 1-adrenoreceptor antagonist: alfuzosin | ↑ alfuzosin | Co-administration is contraindicated due to potential for serious and/or life-threatening reactions such as hypotension.
Antibacterials: clarithromycin, erythromycin, telithromycin | ↑ darunavir ↑ cobicistat ↑ antibacterial | Consider alternative antibiotics with concomitant use of SYMTUZA.
Anticancer agents: dasatinib, nilotinib | ↑ anticancer agent | A decrease in the dosage or an adjustment of the dosing interval of dasatinib or nilotinib may be necessary when co-administered with SYMTUZA. Consult the dasatinib and nilotinib prescribing information for dosing instructions.
vinblastine, vincristine |  | For vincristine and vinblastine, consider temporarily withholding the cobicistat-containing antiretroviral regimen in patients who develop significant hematologic or gastrointestinal side effects when SYMTUZA is administered concurrently with vincristine or vinblastine. If the antiretroviral regimen must be withheld for a prolonged period, consider initiating a revised regimen that does not include a CYP3A or P-gp inhibitor.
Anticoagulants: Direct Oral Anticoagulants (DOACs) apixaban | ↑ apixaban | Due to potentially increased bleeding risk, dosing recommendations for co-administration of apixaban with SYMTUZA depend on the apixaban dose. Refer to apixaban dosing instructions for co-administration with P-gp and strong CYP3A inhibitors in apixaban prescribing information.
rivaroxaban | ↑ rivaroxaban | Co-administration of rivaroxaban with SYMTUZA is not recommended because it may lead to an increased bleeding risk.
dabigatran etexilate edoxaban | ↑ dabigatran ↑ edoxaban | Refer to the dabigatran etexilate or edoxaban prescribing information for recommendations regarding co-administration. The specific recommendations are based on indication, renal function, and effect of the co-administered P-gp inhibitors on the concentration of dabigatran or edoxaban. Clinical monitoring is recommended when a DOAC not affected by CYP3A4 but transported by P-gp, including dabigatran etexilate and edoxaban, is co-administered with SYMTUZA.
Other Anticoagulants
warfarin | warfarin: effect unknown | Monitor international normalized ratio (INR) upon co-administration of SYMTUZA with warfarin.
Anticonvulsants: carbamazepine, phenobarbital, phenytoin | ↓ cobicistat ↓ darunavir ↓ tenofovir alafenamide | Co-administration is contraindicated due to potential for loss of therapeutic effect and development of resistance.
Anticonvulsants with CYP3A induction effects that are NOT contraindicated: e.g., eslicarbazepine, oxcarbazepine | ↓ cobicistat ↓ tenofovir alafenamide darunavir: effect unknown | Consider alternative anticonvulsant or antiretroviral therapy to avoid potential changes in exposures. If co-administration is necessary, monitor for lack or loss of virologic response.
Anticonvulsants that are metabolized by CYP3A: e.g., clonazepam | ↑ clonazepam | Clinical monitoring of anticonvulsants is recommended.
Antidepressants: Selective Serotonin Reuptake Inhibitors (SSRIs): e.g., paroxetine, sertraline | SSRIs: effects unknown | When co-administering with SSRIs, TCAs, or trazodone, careful dose titration of the antidepressant to the desired effect, including using the lowest feasible initial or maintenance dose, and monitoring for antidepressant response are recommended.
Tricyclic Antidepressants (TCAs): e.g., amitriptyline, desipramine, imipramine, nortriptyline | ↑ TCAs
Other antidepressants: trazodone | ↑ trazodone
Antifungals: itraconazole, isavuconazole, ketoconazole, posaconazole | ↑ darunavir ↑ cobicistat | Monitor for increased darunavir or cobicistat and/or antifungal adverse reactions.
 | ↑ itraconazole ↑ isavuconazole ↑ ketoconazole ↔ posaconazole (not studied) | Specific dosing recommendations are not available for co-administration with these antifungals. Monitor for increased itraconazole or ketoconazole adverse reactions.
voriconazole | voriconazole: effects unknown | Co-administration with voriconazole is not recommended unless benefit/risk assessment justifies the use of voriconazole.
Anti-gout: colchicine | ↑ colchicine | Co-administration is contraindicated in patients with renal and/or hepatic impairment due to potential for serious and/or life-threatening reactions. For patients without renal or hepatic impairment:; - Treatment of gout flares – co-administration of colchicine:0.6 mg (1 tablet) ×1 dose, followed by 0.3 mg (half tablet) 1 hour later. Treatment course to be repeated no earlier than 3 days. - Prophylaxis of gout flares – co-administration of colchicine:If the original regimen was 0.6 mg twice a day, the regimen should be adjusted to 0.3 mg once a day. If the original regimen was 0.6 mg once a day, the regimen should be adjusted to 0.3 mg once every other day. - Treatment of familial Mediterranean fever – co-administration of colchicine:Maximum daily dose of 0.6 mg (may be given as 0.3 mg twice a day).
Antimalarial: artemether/lumefantrine | artemether: effect unknown lumefantrine: effect unknown | Monitor for a potential decrease of antimalarial efficacy or potential QT prolongation.
Antimycobacterials: rifampin | ↓ cobicistat ↓ darunavir ↓ tenofovir alafenamide | Co-administration is contraindicated due to potential for loss of therapeutic effect and development of resistance.
rifabutin | ↑ rifabutin ↓ TAF cobicistat: effects unknown darunavir: effects unknown | Co-administration of SYMTUZA with rifabutin is not recommended. If the combination is needed, the recommended dose of rifabutin is 150 mg every other day. Monitor for rifabutin-associated adverse reactions including neutropenia and uveitis.
rifapentine | ↓ darunavir ↓ TAF | Co-administration with rifapentine is not recommended.
Antipsychotics: lurasidone | ↑ lurasidone | Co-administration is contraindicated due to potential for serious and/or life-threatening reactions.
pimozide | ↑ pimozide | Co-administration is contraindicated due to potential for serious and/or life-threatening reactions such as cardiac arrhythmias.
e.g., perphenazine, risperidone, thioridazine | ↑ antipsychotic | A decrease in the dose of antipsychotics that are metabolized by CYP3A or CYP2D6 may be needed when co-administered with SYMTUZA.
quetiapine | ↑ quetiapine | Initiation of SYMTUZA in patients taking quetiapine:Consider alternative antiretroviral therapy to avoid increases in quetiapine exposure. If co-administration is necessary, reduce the quetiapine dose to 1/6 of the current dose and monitor for quetiapine-associated adverse reactions. Refer to the quetiapine prescribing information for recommendations on adverse reaction monitoring. Initiation of quetiapine in patients taking SYMTUZA:Refer to the quetiapine prescribing information for initial dosing and titration of quetiapine.
β-Blockers: e.g., carvedilol, metoprolol, timolol | ↑ beta-blockers | Clinical monitoring is recommended for co-administration with beta-blockers that are metabolized by CYP2D6.
Calcium channel blockers: e.g., amlodipine, diltiazem, felodipine, nifedipine, verapamil | ↑ calcium channel blockers | Clinical monitoring is recommended for co-administration with calcium channel blockers metabolized by CYP3A.
Cardiac Disorders:
ranolazine, ivabradine | ↑ ranolazine | Co-administration is contraindicated due to potential for serious and/or life-threatening reactions.
dronedarone | ↑ dronedarone | Co-administration is contraindicated due to potential for serious and/or life-threatening reactions such as cardiac arrhythmias
Other antiarrhythmics e.g., amiodarone, disopyramide, flecainide, lidocaine (systemic), mexiletine, propafenone, quinidine | ↑ antiarrhythmics | Clinical monitoring is recommended upon co-administration with antiarrhythmics.
digoxin | ↑ digoxin | When co-administering with digoxin, titrate the digoxin dose and monitor digoxin concentrations.
Corticosteroids: dexamethasone (systemic) | ↓ darunavir ↓ cobicistat | Co-administration with systemic dexamethasone or other systemic corticosteroids that induce CYP3A may result in loss of therapeutic effect and development of resistance to SYMTUZA. Consider alternative corticosteroids.
Corticosteroids primarily metabolized by CYP3A: e.g., betamethasone budesonide ciclesonide fluticasone methylprednisolone mometasone triamcinolone | ↑ corticosteroids | Co-administration with corticosteroids (all routes of administration) of which exposures are significantly increased by strong CYP3A inhibitors can increase the risk for Cushing's syndrome and adrenal suppression. Alternative corticosteroids including beclomethasone, prednisone, and prednisolone (for which PK and/or PD are less affected by strong CYP3A inhibitors relative to other steroids) should be considered, particularly for long term use.
Endothelin receptor antagonists: bosentan | ↓ darunavir ↓ cobicistat ↑ bosentan | Initiation of bosentan in patients taking SYMTUZA: In patients who have been receiving SYMTUZA for at least 10 days, start bosentan at 62.5 mg once daily or every other day based upon individual tolerability. Initiation of SYMTUZA in patients on bosentan:Discontinue use of bosentan at least 36 hours prior to initiation of SYMTUZA. After at least 10 days following the initiation of SYMTUZA, resume bosentan at 62.5 mg once daily or every other day based upon individual tolerability. Switching from darunavir co-administered with ritonavir to SYMTUZA in patients on bosentan:Maintain bosentan dose.
Ergot derivatives:
e.g., dihydroergotamine, ergotamine, methylergonovine | ↑ ergot derivatives | Co-administration is contraindicated due to potential for serious and/or life-threatening reactions such as acute ergot toxicity characterized by peripheral vasospasm and ischemia of the extremities and other tissues.
Hepatitis C virus (HCV): Direct-Acting Antivirals:
elbasvir/grazoprevir | ↑ elbasvir/grazoprevir | Co-administration is contraindicated due to potential for the increased risk of alanine transaminase (ALT) elevations.
glecaprevir/pibrentasvir | ↑ glecaprevir ↑ pibrentasvir | Co-administration of SYTMUZA with glecaprevir/pibrentasvir is not recommended.
Herbal product:
St. John's wort (Hypericum perforatum) | ↓ cobicistat ↓ darunavir ↓ tenofovir alafenamide | Co-administration is contraindicated due to potential for loss of therapeutic effect and development of resistance.
Hormonal contraceptives: |  | Additional or alternative (non-hormonal) forms of contraception should be considered when estrogen based contraceptives are co-administered with SYMTUZA.
drosperinone/ethinylestradiol | ↑ drosperinone ↓ ethinylestradiol | For co-administration with drospirenone, clinical monitoring is recommended due to the potential for hyperkalemia.
other progestin/estrogen contraceptives | progestin: effects unknown estrogen: effects unknown | No data are available to make recommendations on co-administration with oral or other hormonal contraceptives.
Immunosuppressants: cyclosporine, sirolimus, tacrolimus | ↑ immunosuppressants | These immunosuppressant agents are metabolized by CYP3A. Therapeutic drug monitoring is recommended with concomitant use.
Immunosuppressant /neoplastic: everolimus |  | Co-administration of everolimus and SYMTUZA is not recommended.
irinotecan |  | Discontinue SYMTUZA at least 1 week prior to starting irinotecan therapy. Do not administer SYMTUZA with irinotecan unless there are no therapeutic alternatives.
Inhaled beta agonist:
salmeterol | ↑ salmeterol | Co-administration with salmeterol is not recommended and may result in increased risk of cardiovascular adverse events associated with salmeterol, including QT prolongation, palpitations, and sinus tachycardia.
Lipid modifying agents: HMG-CoA reductase inhibitors:
lovastatin, simvastatin | ↑ lovastatin ↑ simvastatin | Co-administration is contraindicated due to potential for serious reactions such as myopathy including rhabdomyolysis.
e.g., atorvastatin, fluvastatin, pitavastatin, pravastatin, rosuvastatin | ↑ atorvastatin ↑ fluvastatin ↑ pravastatin ↑ rosuvastatin pitavastatin: effect unknown | For atorvastatin, fluvastatin, pitavastatin, pravastatin, and rosuvastatin, start with the lowest recommended dose and titrate while monitoring for safety.
 |  | Dosage recommendations with atorvastatin or rosuvastatin are as follows:; - atorvastatin dosage should not exceed 20 mg/day - rosuvastatin dosage should not exceed 20 mg/day
Other lipid modifying agents: lomitapide | ↑ lomitapide | Co-administration is contraindicated due to potential for markedly increased transaminases associated with increased plasma concentrations of lomitapide.
Narcotic analgesics metabolized by CYP3A: e.g., fentanyl, oxycodone | ↑ fentanyl ↑ oxycodone | Careful monitoring of therapeutic effects and adverse reactions associated with CYP3A-metabolized narcotic analgesics (including potentially fatal respiratory depression) is recommended with co-administration.
tramadol | ↑ tramadol | A dose decrease may be needed for tramadol with concomitant use.
Narcotic analgesic for treatment of opioid dependence: buprenorphine, buprenorphine/naloxone, methadone | buprenorphine or buprenorphine/ naloxone: effects unknown methadone: effects unknown | Initiation of buprenorphine, buprenorphine/naloxone or methadone in patients taking SYMTUZA:Carefully titrate the dose of buprenorphine, buprenorphine/naloxone or methadone to the desired effect; use the lowest feasible initial or maintenance dose. Initiation of SYMTUZA in patients taking buprenorphine, buprenorphine/naloxone, or methadone:A dose adjustment for buprenorphine, buprenorphine/naloxone, or methadone may be needed. Monitor clinical signs and symptoms.
Opioid Antagonist
naloxegol | ↑ naloxegol | Co-administration of SYMTUZA and naloxegol is contraindicated due to potential for precipitating opioid withdrawal symptoms.
Phosphodiesterase PDE-5 inhibitors: | ↑ PDE-5 inhibitors
e.g., avanafil, sildenafil, tadalafil, vardenafil |  | Co-administration with avanafil is not recommended because a safe and effective avanafil dosage regimen has not been established. Co-administration with PDE-5 inhibitors may result in an increase in PDE-5 inhibitor-associated adverse reactions including hypotension, syncope, visual disturbances, and priapism. Use of PDE-5 inhibitors for pulmonary arterial hypertension (PAH): Co-administration with sildenafil used for PAH is contraindicated due to potential for sildenafil associated adverse reactions (which include visual disturbances, hypotension, prolonged erection, and syncope). The following dose adjustments are recommended for use of tadalafil with SYMTUZA:; - Initiation of tadalafil in patients taking SYMTUZA:In patients receiving SYMTUZA for at least one week, start tadalafil at 20 mg once daily. Increase to 40 mg once daily based upon individual tolerability. - Initiation of SYMTUZA in patients taking tadalafil:Avoid use of tadalafil during the initiation of SYMTUZA. Stop tadalafil at least 24 hours prior to starting SYMTUZA. After at least one week following the initiation of SYMTUZA, resume tadalafil at 20 mg once daily. Increase to 40 mg once daily based upon individual tolerability. - Patients switching from darunavir co-administered with ritonavir to SYMTUZA:Maintain tadalafil dose.; Use of PDE-5 inhibitors for erectile dysfunction: Sildenafil at a single dose not exceeding 25 mg in 48 hours, vardenafil at a single dose not exceeding 2.5 mg dose in 72 hours, or tadalafil at a single dose not exceeding 10 mg dose in 72 hours can be used with increased monitoring for PDE-5 inhibitor-associated adverse reactions.
Platelet aggregation inhibitor: ticagrelor | ↑ticagrelor | Co-administration of SYMTUZA and ticagrelor is not recommended.
clopidogrel | ↓ clopidogrel active metabolite | Co-administration of SYMTUZA and clopidogrel is not recommended due to potential reduction of the antiplatelet activity of clopidogrel.
prasugrel | ↔ prasugrel active metabolite | No dose adjustment is needed when prasugrel is co-administered with SYMTUZA.
Sedatives/hypnotics: orally administered midazolam, triazolam | ↑ midazolam ↑ triazolam | Co-administration is contraindicated due to potential for serious and/or life-threatening reactions such as prolonged or increased sedation or respiratory depression.
metabolized by CYP3A: e.g., buspirone, diazepam, estazolam, zolpidem | ↑ sedatives/hypnotics | With concomitant use, titration is recommended with sedatives/hypnotics metabolized by CYP3A and a lower dose of the sedatives/hypnotics should be considered with monitoring for increased and prolonged effects or adverse reactions.
parenterally administered midazolam |  | Co-administration of parenteral midazolam should be done in a setting that ensures close clinical monitoring and appropriate medical management in case of respiratory depression and/or prolonged sedation. Dose reduction for parenteral midazolam should be considered, especially if more than a single dose of midazolam is administered.
Urinary antispasmodics
fesoterodine | ↑ fesoterodine | When fesoterodine is co-administered with SYMTUZA, do not exceed a fesoterodine dose of 4 mg once daily.
solifenacin | ↑ solifenacin | When solifenacin is co-administered with SYMTUZA, do not exceed a solifenacin dose of 5 mg once daily.
This table is not all inclusive
↑ = increase, ↓ = decrease, ↔ = no effect

8. USE IN SPECIFIC POPULATIONS

8.1 Pregnancy

Pregnancy Exposure Registry

There is a pregnancy exposure registry that monitors pregnancy outcomes in individuals exposed to SYMTUZA during pregnancy. Healthcare providers are encouraged to register patients by calling the Antiretroviral Pregnancy Registry (APR) at 1-800-258-4263.

Risk Summary

SYMTUZA is not recommended during pregnancy because of substantially lower exposures of darunavir and cobicistat during the second and third trimesters [see Dosage and Administration (2.5)] . A study evaluating the pharmacokinetics of antiretrovirals during pregnancy demonstrated substantially lower exposures of darunavir and cobicistat in the second and third trimesters compared to the post-partum period (see Data) and [see Clinical Pharmacology (12.3)].

Prospective pregnancy data from the APR are not sufficient to adequately assess the risk of birth defects or miscarriage. However, available data from the APR show no statistically significant difference in the overall risk of major birth defects for darunavir, cobicistat, emtricitabine, or tenofovir alafenamide (TAF) compared with the background rate for major birth defects of 2.7% in a U.S. reference population of the Metropolitan Atlanta Congenital Defects Program (MACDP) (see Data) . The rate of miscarriage is not reported in the APR. The estimated background rate of miscarriage in clinically recognized pregnancies in the U.S. general population is 15–20%. The background risk of major birth defects and miscarriage for the indicated population is unknown.

In animal reproduction studies, no adverse developmental effects were observed when the components of SYMTUZA were administered separately at darunavir exposures less than 1- (mice and rabbits) and 2.6-times (rats) higher, at cobicistat exposures 1.7- and 4.1-times higher (rats and rabbits respectively), at emtricitabine exposures 88- and 7.3- times higher (mice and rabbits, respectively), and tenofovir alafenamide exposures equal to or 85- times higher (rats and rabbits, respectively) than human exposures at the recommended daily dose of these components in SYMTUZA (see Data) . No adverse developmental effects were seen when cobicistat was administered to rats through lactation at cobicistat exposures up to 1.1 times the human exposure at the recommended therapeutic dose.

Clinical Considerations

Not Recommended During Pregnancy

SYMTUZA is not recommended for use during pregnancy because of substantially lower exposures of darunavir and cobicistat during pregnancy (see Data) and [see Clinical Pharmacology (12.3)] .

SYMTUZA should not be initiated in pregnant individuals. An alternative regimen is recommended for individuals who become pregnant during therapy with SYMTUZA.

Data

Human Data

Darunavir and cobicistat in combination with a background regimen was evaluated in a clinical trial of 7 pregnant individuals taking darunavir and cobicistat prior to enrollment and who were willing to remain on darunavir and cobicistat throughout the study. The study period included the second and third trimesters, and through 12 weeks postpartum. Six pregnant individuals completed the trial.

Exposure to darunavir and cobicistat as part of an antiretroviral regimen was substantially lower during the second and third trimesters of pregnancy compared with postpartum [see Clinical Pharmacology (12.3)] .

One out of 6 pregnant individuals who completed the study experienced virologic failure with HIV-1 RNA >1,000 copies/mL from the third trimester visit through the postpartum period. Five pregnant individuals had sustained virologic response (HIV RNA <50 copies/mL) throughout the study period. There are no clinical data on the virologic response when darunavir and cobicistat are initiated during pregnancy.

Prospective reports from the APR of overall major birth defects in pregnancies exposed to the components of SYMTUZA are compared with a U.S. background major birth defect rate. Methodological limitations of the APR include the use of MACDP as the external comparator group. Limitations of using an external comparator include differences in methodology and populations, as well as confounding due to the underlying disease.

Darunavir: Based on prospective reports to the APR of over 960 exposures to darunavir-containing regimens during pregnancy resulting in live births (including over 640 exposed in the first trimester and over 320 exposed in the second/third trimester), the prevalence of birth defects in live births was 3.7% (95% CI: 2.4% to 5.5%) with first trimester exposure to darunavir containing-regimens and 2.5% (95% CI: 1.1% to 4.9%) with second/third trimester exposure to darunavir-containing regimens.

Cobicistat: Based on prospective reports to the APR of over 560 exposures to cobicistat-containing regimens during pregnancy resulting in live births (including over 470 exposed in the first trimester and over 80 exposed in the second/third trimester), the prevalence of birth defects in live births was 3.6% (95% CI: 2.1% to 5.7%) and 1.1% (95% CI: 0.0% to 6.2%) with first and second/third trimester, respectively, to cobicistat-containing regimens.

Emtricitabine: Based on prospective reports to the APR of over 5400 exposures to emtricitabine-containing regimens during pregnancy resulting in live births (including over 3900 exposed in the first trimester and over 1500 exposed in the second/third trimester), the prevalence of birth defects in live births was 2.6% (95% CI: 2.2% to 3.2%) with first trimester exposure to emtricitabine-containing regimens and 2.7% (95% CI: 1.9% to 3.7%) with the second/third trimester exposure to emtricitabine-containing regimens.

Tenofovir alafenamide (TAF): Based on prospective reports to the APR of over 660 exposures to TAF-containing regimens during pregnancy resulting in live births (including over 520 exposed in the first trimester and over 130 exposed in the second/third trimester), the prevalence of birth defects in live births was 4.2% (95% CI: 2.6% to 6.3%) and 3.0% (95% CI: 0.8% to 7.5%) with first and second/third trimester exposure, respectively, to TAF-containing regimens.

Animal Data

Darunavir: Reproduction studies conducted with darunavir showed no embryotoxicity or teratogenicity in mice (doses up to 1000 mg/kg from gestation day (GD) 6–15 with darunavir alone) and rats (doses up to 1000 mg/kg from GD 7–19 in the presence or absence of ritonavir) as well as in rabbits (doses up to 1000 mg/kg/day from GD 8–20 with darunavir alone). In these studies, darunavir exposures (based on AUC) were higher in rats (2.6-fold), whereas in mice and rabbits, exposures were lower (less than 1-fold) compared to those obtained in humans at the recommended daily dose of darunavir in SYMTUZA.

Cobicistat: Cobicistat was administered orally to pregnant rats at doses up to 125 mg/kg/day on GD 6–17. Increases in post-implantation loss and decreased fetal weights were observed at a maternal toxic dose of 125 mg/kg/day. No malformations were noted at doses up to 125 mg/kg/day. Systemic exposures (AUC) at 50 mg/kg/day in pregnant females were 1.7 times higher than human exposures at the recommended daily dose of cobicistat in SYMTUZA.

In pregnant rabbits, cobicistat was administered orally at doses up to 100 mg/kg/day during GD 7–20. No maternal or embryo/fetal effects were noted at the highest dose of 100 mg/kg/day. Systemic exposures (AUC) at 100 mg/kg/day were 4.1 times higher than human exposures at the recommended daily dose of cobicistat in SYMTUZA.

In a pre/postnatal developmental study in rats, cobicistat was administered orally at doses up to 75 mg/kg from GD 6 to postnatal day 20, 21, or 22. At doses of 75 mg/kg/day, neither maternal nor developmental toxicity was noted. Systemic exposures (AUC) at this dose were 1.1 times the human exposures at the recommended daily dose of cobicistat in SYMTUZA.

Emtricitabine: Emtricitabine was administered orally to pregnant mice and rabbits (up to 1000 mg/kg/day) through organogenesis (on GD 6 through 15, and 7 through 19, respectively). No significant toxicological effects were observed in embryo-fetal toxicity studies performed with emtricitabine in mice at exposures approximately 88 times higher and in rabbits approximately 7.3 times higher than human exposures at the recommended daily dose of emtricitabine in SYMTUZA.

In a pre/postnatal development study, mice were administered doses up to 1000 mg/kg/day; no significant adverse effects directly related to drug were observed in the offspring exposed daily from before birth (in utero) through sexual maturity at daily exposures of approximately 88 times higher than human exposures at the recommended daily dose of emtricitabine in SYMTUZA.

Tenofovir Alafenamide (TAF): TAF was administered orally to pregnant rats (up to 250 mg/kg/day) and rabbits (up to 100 mg/kg/day) through organogenesis (on GD 6 through 17, and 7 through 20, respectively). No adverse embryo-fetal effects were observed in rats and rabbits at TAF exposures approximately similar to (rats) and 85 times higher (rabbits) than the exposure in humans at the recommended daily dose. TAF is rapidly converted to tenofovir; the observed tenofovir exposure in rats and rabbits were 51 (rats) and 80 (rabbits) times higher than human tenofovir exposures at the recommended daily dose of TAF in SYMTUZA.

Since TAF is rapidly converted to tenofovir and a lower tenofovir exposure in rats and mice was observed after TAF administration compared to TDF (another prodrug of tenofovir) administration, a pre/postnatal development study in rats was conducted only with TDF. Doses up to 600 mg/kg/day were administered through lactation; no adverse effects were observed in the offspring on GD 7 [and lactation day 20] at tenofovir exposures of approximately 14 [21] times higher than the exposure in humans at the recommended daily dose of TDF.

8.2 Lactation

Risk Summary

The Centers for Disease Control and Prevention recommend that HIV-infected mothers in the United States must not breastfeed their infants to avoid risking postnatal transmission of HIV-1 infection.

Based on published data, emtricitabine has been shown to be present in human breast milk. There are no data on the presence of darunavir, cobicistat, or TAF in human milk, the effects on the breastfed infant, or the effects on milk production. Darunavir and cobicistat are present in the milk of lactating rats. Tenofovir has been shown to be present in the milk of lactating rats and rhesus monkeys after administration of TDF (see Data) . Because of the potential for (1) HIV transmission (in HIV-negative infants), (2) developing viral resistance (in HIV-positive infants), and (3) serious adverse reactions in breastfed infants, instruct mothers not to breastfeed if they are receiving SYMTUZA.

Data

Animal Data

Darunavir: Studies in rats (with darunavir alone or with ritonavir) have demonstrated that darunavir is excreted in milk. In the rat pre- and post-natal development study, a reduction in pup body weight gain was observed due to exposure of pups to drug substances via milk. The maximal maternal plasma exposures achieved with darunavir (up to 1000 mg/kg with ritonavir) were approximately 66% of those obtained in humans at the recommended clinical dose of darunavir with ritonavir.

Cobicistat: During the pre/postnatal developmental toxicology study, at doses up to 75 mg/kg/day, mean cobicistat milk to plasma ratio of up to 1.9 was measured 2 hours after administration to rats on lactation day 10.

Tenofovir Alafenamide: Studies in rats and monkeys have demonstrated that tenofovir is excreted in milk. Tenofovir was excreted into the milk of lactating rats following oral administration of TDF (up to 600 mg/kg/day) at up to approximately 24% of the median plasma concentration in the highest dosed animals at lactation day 11. Tenofovir was excreted into the milk of lactating rhesus monkeys, following a single subcutaneous (30 mg/kg) dose of tenofovir at concentrations up to approximately 4% of plasma concentration resulting in exposure (AUC) of approximately 20% of plasma exposure.

8.4 Pediatric Use

The safety and effectiveness of SYMTUZA for the treatment of HIV-1 infection in pediatric patients weighing at least 40 kg was established through studies with components of SYMTUZA. Use of SYMTUZA in this group is supported by evidence from adequate and well-controlled studies of SYMTUZA in adults with additional pharmacokinetic, safety, and virologic data from studies of components of SYMTUZA (Trials GS-US-216-0128 and GS-US-292-0106) in pediatric subjects with HIV-1 infection aged 12 to less than 18 years [see Adverse Reactions (6.1), Clinical Pharmacology (12.3), and Clinical Studies (14.3)] .

The safety and effectiveness of SYMTUZA have not been established in pediatric patients weighing less than 40 kg.

Darunavir, a component of SYMTUZA is not recommended in pediatric patients below 3 years of age because of toxicity and mortality observed in juvenile rats dosed with darunavir.

Juvenile Animal Toxicity Data

Darunavir: In a juvenile toxicity study where rats were directly dosed with darunavir (up to 1000 mg/kg), deaths occurred from post-natal day 5 at plasma exposure levels ranging from 0.1 to 1.0 of the human exposure levels. In a 4-week rat toxicology study, when dosing was initiated on post-natal day 23 (the human equivalent of 2 to 3 years of age), no deaths were observed with a plasma exposure (in combination with ritonavir) 2 times the human plasma exposure levels.

8.5 Geriatric Use

Clinical trials of SYMTUZA included 35 subjects aged above 65 years of which 26 received SYMTUZA. No differences in safety or efficacy have been observed between elderly subjects and those aged 65 years or less. In general, caution should be exercised in the administration and monitoring of SYMTUZA in elderly patients, reflecting the greater frequency of decreased hepatic function and of concomitant disease or other drug therapy [see Clinical Pharmacology (12.3)] .

8.6 Renal Impairment

SYMTUZA is not recommended in patients with severe renal impairment (creatinine clearance below 30 mL per minute). No dosage adjustment of SYMTUZA is required in patients with creatinine clearance greater than or equal to 30 mL per minute [see Clinical Pharmacology (12.3)] .

Cobicistat has been shown to decrease creatinine clearance without affecting actual renal glomerular function. Dosing recommendations are not available for drugs that require dosage adjustment for renal impairment when used in combination with SYMTUZA [see Warnings and Precautions (5.6)] .

8.7 Hepatic Impairment

No dosage adjustment of SYMTUZA is required in patients with mild (Child-Pugh Class A) or moderate (Child-Pugh Class B) hepatic impairment. SYMTUZA has not been studied in patients with severe hepatic impairment (Child-Pugh Class C) and there are only limited data regarding the use of SYMTUZA components in this population. Therefore, SYMTUZA is not recommended for use in patients with severe hepatic impairment [see Clinical Pharmacology (12.3)] .

10. OVERDOSAGE

Human experience of acute overdose with SYMTUZA is limited. There is no specific antidote for overdose with SYMTUZA. Treatment of overdose with SYMTUZA consists of general supportive measures including monitoring of vital signs and observation of the clinical status of the patient.

Since darunavir and cobicistat are highly bound to plasma proteins, it is unlikely that they will be significantly removed by hemodialysis or peritoneal dialysis. Hemodialysis treatment removes approximately 30% of the emtricitabine dose over a 3-hour dialysis period starting within 1.5 hours of emtricitabine dosing (blood flow rate of 400 mL/min and a dialysate flow rate of 600 mL/min). Tenofovir is efficiently removed by hemodialysis with an extraction coefficient of approximately 54%. It is not known whether emtricitabine or tenofovir can be removed by peritoneal dialysis.

11. DESCRIPTION

SYMTUZA®(darunavir, cobicistat, emtricitabine, and tenofovir alafenamide) is a fixed-dose combination tablet.

- Darunavir is an inhibitor of the HIV-1 protease.
- Cobicistat is a mechanism-based inhibitor of cytochrome P450 (CYP) enzymes of the CYP3A family.
- Emtricitabine, a synthetic nucleoside analog of cytidine, is an HIV nucleoside analog reverse transcriptase inhibitor (HIV NRTI).
- Tenofovir alafenamide, an HIV NRTI, is converted in vivoto tenofovir, an acyclic nucleoside phosphonate (nucleotide) analog of adenosine 5′-monophosphate.

SYMTUZA tablets are for oral administration. Each tablet contains darunavir ethanolate equivalent to 800 mg of darunavir, 150 mg of cobicistat, 200 mg of emtricitabine, and 11.2 mg of tenofovir alafenamide fumarate equivalent to 10 mg of tenofovir alafenamide. The tablets include the following inactive ingredients: colloidal silicon dioxide, croscarmellose sodium, magnesium stearate, and microcrystalline cellulose. The tablets are film-coated with a coating material containing polyethylene glycol (macrogol), polyvinyl alcohol (partially hydrolyzed), talc, titanium dioxide, and yellow ferric oxide.

Darunavir: Darunavir, in the form of darunavir ethanolate, has the following chemical name: [(1 S,2 R)-3-[[(4-aminophenyl)sulfonyl](2-methylpropyl)amino]-2-hydroxy-1-(phenylmethyl)propyl]-carbamic acid (3 R,3a S,6a R)-hexahydrofuro[2,3- b]furan-3-yl ester monoethanolate. Its molecular formula is C27H37N3O7S ∙ C2H5OH and its molecular weight is 593.73. Darunavir ethanolate has the following structural formula:

Cobicistat: Cobicistat is adsorbed onto silicon dioxide. The chemical name for cobicistat is 1,3-thiazol-5-ylmethyl[(2 R,5 R)-5-{[(2 S)-2-[(methyl{[2-(propan-2-yl)-1,3-thiazol-4-yl]methyl}carbamoyl)amino]-4-(morpholin-4yl)butanoyl]amino}-1,6-diphenylhexan-2-yl]carbamate. It has a molecular formula of C40H53N7O5S2and a molecular weight of 776.02. It has the following structural formula:

Emtricitabine: The chemical name of emtricitabine is 4-amino-5-fluoro-1-(2 R-hydroxymethyl-[1,3]-oxathiolan-5 S-yl)-(1H)-pyrimidin-2-one. Emtricitabine is the (-)enantiomer of a thio analog of cytidine, which differs from other cytidine analogs in that it has a fluorine in the 5 position. Emtricitabine has a molecular formula of C8H10FN3O3S and a molecular weight of 247.24. It has the following structural formula:

Tenofovir alafenamide: The chemical name of tenofovir alafenamide fumarate drug substance is L-alanine, N-[(S)-[[(1 R)-2-(6-amino-9 H-purin-9-yl)-1-methylethoxy]methyl]phenoxyphosphinyl]-,1-methylethyl ester, (2 E)-2-butenedioate (2:1). Tenofovir alafenamide fumarate has a molecular formula of C21H29O5N6P∙½(C4H4O4) and a formula weight of 534.50. It has the following structural formula:

12. CLINICAL PHARMACOLOGY

12.1 Mechanism of Action

SYMTUZA is a fixed-dose combination of antiretroviral drugs darunavir (plus the CYP3A inhibitor cobicistat), emtricitabine, and tenofovir alafenamide [see Microbiology (12.4)] .

12.2 Pharmacodynamics

Cardiac Electrophysiology

Thorough QT trials have been conducted for darunavir, cobicistat, and tenofovir alafenamide. The effect of emtricitabine or the combination regimen SYMTUZA on the QT interval has not been evaluated.

Darunavir: In a thorough QT/QTc study in 40 healthy subjects, darunavir doses (co-administered with 100 mg ritonavir) of approximately 2 times the recommended darunavir dose did not affect the QT/QTc interval.

Cobicistat: In a thorough QT/QTc study in 48 healthy subjects, a single dose of cobicistat 250 mg and 400 mg (1.67 and 2.67 times the dose in SYMTUZA) did not affect the QT/QTc interval. Prolongation of the PR interval was noted in subjects receiving cobicistat. The maximum mean (95% upper confidence bound) difference in PR from placebo after baseline-correction was 9.5 (12.1) msec for the 250 mg cobicistat dose and 20.2 (22.8) for the 400 mg cobicistat dose. Because the 150 mg cobicistat dose used in the SYMTUZA fixed-dose combination tablet is lower than the lowest dose studied in the thorough QT study, it is unlikely that treatment with SYMTUZA will result in clinically relevant PR prolongation.

Tenofovir alafenamide: In a thorough QT/QTc study in 48 healthy subjects, tenofovir alafenamide at the recommended dose or at a dose approximately 5 times the recommended dose did not affect the QT/QTc interval and did not prolong the PR interval.

Effects on Serum Creatinine

The effect of cobicistat on serum creatinine was investigated in a trial in subjects with normal renal function (eGFRCG≥80 mL/min, N=12) and mild-to-moderate renal impairment (eGFRCG50–79 mL/min, N=18). A statistically significant decrease from baseline in the estimated glomerular filtration rate calculated by Cockcroft-Gault method (eGFRCG) was observed after 7 days of treatment with cobicistat 150 mg among subjects with normal renal function (-9.9 ± 13.1 mL/min) and mild-to-moderate renal impairment (-11.9 ± 7.0 mL/min). No statistically significant changes in eGFRCGwere observed compared to baseline for subjects with normal renal function or mild-to-moderate renal impairment 7 days after cobicistat was discontinued. The actual glomerular filtration rate, as determined by the clearance of probe drug iohexol, was not altered from baseline during treatment with cobicistat among subjects with normal renal function and mild-to-moderate renal impairment, indicating that cobicistat inhibits tubular secretion of creatinine, reflected as a reduction in eGFRCG, without affecting the actual glomerular filtration rate.

12.3 Pharmacokinetics

Absorption, Distribution, Metabolism, and Excretion

The bioavailability of the components of SYMTUZA was not affected when administered orally as a split tablet compared to administration as a tablet swallowed whole.

Pharmacokinetic (PK) properties and PK parameters of the components of SYMTUZA are provided in Table 5 and Table 6, respectively.

Table 5: Pharmacokinetic Properties of the Components of SYMTUZA
 | Darunavir | Cobicistat | Emtricitabine | TAF
Absorption
Tmax(h) | 3.0 | 3.0 | 1.5 | 0.5
Effect of high-fat meal [Approximately 928 kcal; 504 kcal from fat (56 g), 260 kcal from carbohydrates, and 164 kcal from protein.] (compared to fasting)
AUClastLS mean ratio, 90% CI | 1.52 (1.32–1.76) | 1.41 (1.02–1.96) | 1.00 (0.96–1.04) | 1.12 (1.01–1.23)
CmaxLS mean ratio, 90% CI | 1.82 (1.55–2.14) | 1.30 (0.94–1.80) | 0.79 (0.71–0.89) | 0.55 (0.42–0.71)
Distribution
% bound to human plasma proteins | 95 [Primarily alpha-1-acid glycoprotein] | 97–98 | <4 | ~80
Source of protein binding data | In vitro | In vitro | In vitro | Ex vivo
Blood-to-plasma ratio | 0.64 | 0.5 | 0.6 | 1.0
Metabolism
Metabolism | CYP3A | CYP3A (major) CYP2D6 (minor) | Not significantly metabolized | Cathepsin A [In vivo, TAF is hydrolyzed within cells to form tenofovir (major metabolite), which is phosphorylated to the active metabolite, tenofovir diphosphate. In vitro studies have shown that TAF is metabolized to tenofovir by cathepsin A in PBMCs and macrophages; and by CES1 in hepatocytes. Upon co-administration with the moderate CYP3A inducer probe efavirenz, TAF exposure was unaffected.] (PBMCs) CES1 (hepatocytes) CYP3A (minimal)
Elimination
t1/2(h) | 9.4 | 3.2 | 7.5 | 0.5 [Note that the pharmacologically active metabolite tenofovir diphosphate has a half-life of 150–180 hours within PBMCs. Tenofovir in plasma has a median elimination half-life of approximately 44 hours.]
Major route of elimination | Metabolism | Metabolism | Glomerular filtration and active tubular secretion | Metabolism (>80% of oral dose)
% of dose excreted in feces [Dosing in mass balance studies: darunavir (single dose administration of [ 14C] darunavir co-administered with multiple dose ritonavir 100 mg); cobicistat (single dose administration of [ 14C] cobicistat after multiple dosing of cobicistat for six days); emtricitabine (single dose administration of [ 14C] emtricitabine after multiple dosing of emtricitabine for ten days); TAF (single dose administration of [ 14C] TAF).] | 79.5 [Unchanged darunavir accounted for approximately 41.2% and 7.7% of the administered dose in feces and urine, respectively.] | 86.2 | 13.7 | 31.7
% of dose excreted in urine | 13.9 | 8.2 | 70 | <1
PBMCs = peripheral blood mononuclear cells; CES-1 = carboxylesterase-1

Table 6: Steady State Pharmacokinetic Parameters of Darunavir, Cobicistat, Emtricitabine, Tenofovir Alafenamide (TAF) and its Metabolite Tenofovir Following Oral Administration of SYMTUZA with Food in HIV-Infected Adults
Parameter Mean (SD) | Darunavir |  | Cobicistat [From Phase 2 PK substudy (N=21)] | Emtricitabine | TAF | Tenofovir
Cmax, ng/mL | 8826 (33.3) |  | 1129 (35.3) | 2056 (25.3) | 163 (51.9) | 18.8 (37.6)
AUC24h, ng.h/mL | 87909 (20232) [From population PK analysis in SYMTUZA Phase 3 study TMC114FD2HTX3001 in ARV naïve subjects (N=355)] | 85972 (22413) [From population PK analysis in SYMTUZA Phase 3 study TMC114IFD3013 in ARV experienced subjects (N=750)] | 8745 (43.9) | 11918.0 (35.9) | 132 (41) | 339 (37.1)
C0h, ng/mL | 1899 (759) | 1813 (859) | 31 (135) | 93.1 (58.3) | NA | 11.7 (39.3)

Specific Populations

Geriatric Patients

Darunavir: Pharmacokinetic analysis in HIV-infected subjects taking darunavir co-administered with cobicistat, emtricitabine, and tenofovir alafenamide showed no considerable differences in darunavir pharmacokinetics for ages below or equal to 65 years compared to ages greater than 65 years (N=25).

Cobicistat and Emtricitabine: The pharmacokinetics of cobicistat and emtricitabine have not been fully evaluated in the elderly (65 years of age and older).

Tenofovir alafenamidePopulation pharmacokinetics analysis of HIV-infected subjects in Phase 2 and Phase 3 trials of TAF combined with emtricitabine, elvitegravir, and cobicistat showed that age did not have a clinically relevant effect on exposures of TAF up to 75 years of age.

Pediatric Patients Weighing at Least 40 kg

Available pharmacokinetic data for the different components of SYMTUZA indicate that there were no clinically relevant differences in exposure between adults and pediatric subjects weighing at least 40 kg.

Darunavir and cobicistat: In pediatric subjects aged 12 to less than 18 years, weighing at least 40 kg who received darunavir 800 mg co-administered with cobicistat 150 mg (N=7), geometric mean darunavir Cmaxvalues were similar between adults and pediatric subjects. Geometric mean darunavir AUC24hand C24hvalues were 15% and 32% lower, with geometric mean ratios of 0.85 (90% CI: 0.64, 1.13) and 0.68 (90% CI: 0.30, 1.55) in pediatric subjects relative to adults, respectively. These differences were not considered clinically significant. Geometric mean cobicistat AUC24h, Cmax, and C24hvalues were comparable in pediatric subjects and adults (Table 7).

Table 7: Multiple-Dose PK Parameters of Darunavir and Cobicistat Following Administration of Darunavir with Cobicistat in HIV 1 Infected Adults and Pediatric Subjects Weighing at least 40 kg [From intensive PK analysis of trial GS-US-216-0128, where HIV-infected subjects were administered darunavir 800 mg and cobicistat 150 mg once daily with 2 NRTIs]
Parameter Geometric mean (CV%) | Darunavir | Cobicistat
Pediatric Subjects | N=7 | N=7
AUC24h(mcg.hr/mL) | 77.22 (29.5) | 8.33 (34.9)
Cmax(mcg/mL) | 7.32 (21.7) | 1.10 (20.0)
C24h(mcg/mL) | 0.68 (91.6) | 0.02 (123.9) [N=5; Data from two subjects who had undetectable cobicistat C 24h concentrations were excluded from summary statistics]
Adults [From intensive PK analysis of trial GS-US-299-0102 where HIV-infected subjects were administered SYMTUZA once daily] | N=21 | N=21
AUC24h(mcg.hr/mL) | 90.56 (45.3) | 7.69 (43.9)
Cmax(mcg/mL) | 8.34 (33.3) | 1.04 (35.3)
C24h(mcg/mL) | 1.00 (108.0) | 0.02 (135.1) [N=18]
CV = Coefficient of Variation; mcg = microgram

Emtricitabine and tenofovir alafenamide: In 24 pediatric subjects aged 12 to less than 18 years, who received emtricitabine + TAF with elvitegravir + cobicistat, geometric mean emtricitabine Cmax, and C24hvalues were comparable to adults, with geometric mean ratios of 1.10 (90% CI: 0.98, 1.23) and 1.07 (90% CI: 0.88, 1.29), respectively (Table 8). Geometric mean emtricitabine AUC24hwas 21% higher, with a geometric mean ratio of 1.21 (90% CI: 1.09, 1.34) in pediatric subjects relative to adults. Geometric mean tenofovir alafenamide Cmaxand AUClastvalues were 29% and 23% lower in pediatric subjects versus adults with geometric mean ratios of 0.71 (90% CI: 0.50, 1.00) and 0.77 (90% CI: 0.59, 1.02), respectively (Table 8). The observed differences were not considered clinically significant.

Table 8: Multiple-Dose PK Parameters of Emtricitabine and Tenofovir Alafenamide Following Oral Administration with Food in HIV 1 Infected Adults and Pediatric Subjects
Parameter Geometric mean (CV%) | Emtricitabine | Tenofovir alafenamide
Pediatric Subjects [From intensive PK analysis in trial GS-US-292-0106 in treatment-naïve pediatric subjects with HIV-1 infection] | N=24 | N=24
AUC24h(mcg.hr/mL) [AUC last for tenofovir alafenamide] | 14.0 (23.9) | 0.16 (55.8)
Cmax(mcg/mL) | 2.2 (22.5) | 0.14 (64.4)
C24h(mcg/mL) | 0.10 (38.9) [N=23] | NA
Adults [From intensive PK analysis in trial GS-US-292-0102 in HIV-infected adults treated with emtricitabine+tenofovir alafenamide and elvitegravir+cobicistat] | N=19 | N=19
AUC24h(mcg.hr/mL) | 11.6 (16.6) | 0.21 (47.3)
Cmax(mcg/mL) | 2.0 (20.2) | 0.19 (64.6)
C24h(mcg/mL) | 0.09 (46.7) | NA
CV = Coefficient of Variation; mcg = microgram; NA = not applicable

Gender and Race

There were no clinically relevant differences in the pharmacokinetics of darunavir, cobicistat, emtricitabine, or tenofovir alafenamide based on gender or race.

Patients with Renal Impairment

Darunavir: The pharmacokinetics of darunavir were not altered in HIV-1 infected subjects with moderate renal impairment taking darunavir co-administered with ritonavir (creatinine clearance between 30–60 mL/min, estimated by Cockcroft-Gault method, N=20). There are no pharmacokinetic data available in HIV-1 infected patients with severe renal impairment or end-stage renal disease taking darunavir co-administered with cobicistat [see Use in Specific Populations (8.6)] .

Cobicistat: There were no clinically relevant differences in cobicistat pharmacokinetics observed between subjects with severe renal impairment (creatinine clearance below 30 mL/min, estimated by Cockcroft-Gault method) and healthy subjects [see Use in Specific Populations (8.6)] .

Emtricitabine: Mean systemic emtricitabine exposure was higher in patients with severe renal impairment (creatinine clearance less than 30 mL/min, estimated by Cockcroft-Gault method) than in subjects with normal renal function [see Use in Specific Populations (8.6)] .

Tenofovir alafenamide: In studies of TAF, no clinically relevant differences in the pharmacokinetics of TAF or its metabolite tenofovir were observed between subjects with severe renal impairment (creatinine clearance of 15–30 mL/min, estimated by Cockcroft-Gault method) and healthy subjects [see Use in Specific Populations (8.6)] .

Patients with Hepatic Impairment

Darunavir: There were no clinically relevant differences in the pharmacokinetics of darunavir (600 mg with ritonavir 100 mg twice daily) in subjects with mild hepatic impairment (Child-Pugh Class A, n=8), and moderate hepatic impairment (Child-Pugh Class B, n=8), compared to subjects with normal hepatic function (n=16). The effect of severe hepatic impairment on the pharmacokinetics of darunavir has not been evaluated [see Use in Specific Populations (8.7)] .

Cobicistat: There were no clinically relevant differences in the cobicistat pharmacokinetics between subjects with moderate hepatic impairment (Child-Pugh Class B) and healthy subjects. The effect of severe hepatic impairment on the pharmacokinetics of cobicistat has not been evaluated [see Use in Specific Populations (8.7)] .

Emtricitabine: The pharmacokinetics of emtricitabine have not been studied in subjects with hepatic impairment; however, emtricitabine is not significantly metabolized by liver enzymes, so the impact of hepatic impairment should be limited [see Use in Specific Populations (8.7)] .

Tenofovir Alafenamide: Clinically relevant changes in the pharmacokinetics of tenofovir alafenamide or its metabolite tenofovir were not observed in patients with mild, moderate (Child-Pugh Class A and B), or severe hepatic impairment (Child-Pugh Class C); [see Use in Specific Populations (8.7)] .

Patients with Hepatitis B and/or Hepatitis C Virus Coinfection

Darunavir: In HIV-infected subjects taking darunavir co-administered with ritonavir, the 48-week analysis of the data from clinical trials indicated that hepatitis B and/or hepatitis C virus coinfection status had no apparent effect on the exposure of darunavir.

Cobicistat: There were insufficient pharmacokinetic data in the clinical trials to determine the effect of hepatitis B and/or C virus infection on the pharmacokinetics of cobicistat.

Emtricitabine and tenofovir alafenamide: The pharmacokinetics of emtricitabine and tenofovir alafenamide have not been fully evaluated in subjects coinfected with hepatitis B and/or C virus.

Pregnancy and Postpartum

The exposure to total and unbound darunavir boosted with cobicistat after intake of darunavir/cobicistat as part of an antiretroviral regimen was substantially lower during the second and third trimesters of pregnancy compared with 6–12 weeks postpartum (see Table 9and Figure 1).

Table 9: Pharmacokinetic Results of Total Darunavir after Administration of Darunavir/Cobicistat Once Daily as Part of an Antiretroviral Regimen, During the 2ndTrimester of Pregnancy, the 3rdTrimester of Pregnancy, and Postpartum
Pharmacokinetics of total darunavir (mean ± SD) | 2ndTrimester of pregnancy N=7 | 3rdTrimester of pregnancy N=6 | Postpartum (6–12 weeks) N=6
Cmax, ng/mL | 4340 ± 1616 | 4910 ± 970 | 7918 ± 2199
AUC24h, ng.h/mL | 47293 ± 19058 | 47991 ± 9879 | 99613 ± 34862
Cmin, ng/mL | 168 ± 149 | 184 ± 99 | 1538 ± 1344

Figure 1: Pharmacokinetic Results (Within-Subject Comparison) of Total and Unbound Darunavir and Total Cobicistat After Administration of Darunavir/Cobicistat at 800/150 mg Once Daily as Part of an Antiretroviral Regimen, During the 2ndand 3rdTrimester of Pregnancy Compared to Postpartum

Legend: 90% CI: 90% confidence interval; GMR: geometric mean ratio (i.e., second or third trimester/postpartum). Solid vertical line: ratio of 1.0; dotted vertical lines: reference lines of 0.8 and 1.25.

Drug Interactions

Darunavir is metabolized by CYP3A. Cobicistat is metabolized by CYP3A and, to a minor extent, by CYP2D6. Darunavir co-administered with cobicistat is an inhibitor of CYP3A and CYP2D6. Cobicistat inhibits the following transporters: P-gp, BCRP, MATE1, OATP1B1, and OATP1B3. Based on in vitrodata, cobicistat is not expected to induce CYP1A2 or CYP2B6 and based on in vivodata, cobicistat is not expected to induce MDR1 or, in general, CYP3A to a clinically significant extent. The induction effect of cobicistat on CYP2C9, CYP2C19, or UGT1A1 is unknown, but is expected to be low based on CYP3A in vitroinduction data.

Emtricitabine is not an inhibitor of human CYP450 enzymes. In vitroand clinical drug interaction studies have shown that the potential for CYP-mediated interactions involving emtricitabine with other medicinal products is low. Tenofovir alafenamide is not an inhibitor of CYP1A2, CYP2B6, CYP2C8, CYP2C9, CYP2C19, CYP2D6, or UGT1A. It is not an inhibitor or inducer of CYP3A in vivo.

A drug-drug interaction study between darunavir/cobicistat and dabigatran etexilate was conducted in healthy participants. The effects of darunavir on co-administration with dabigatran etexilate are summarized in Table 10.

Table 10: Drug Interactions: Pharmacokinetic Parameters for Co-Administered Drugs in the Presence of darunavir/cobicistat
 | Dose/Schedule |  |  |  | LS Mean ratio (90% CI) of co-administered drugpharmacokinetic parameters with/without darunavir no effect =1.00
Co-administered drug | Co-administered drug | Darunavir/ cobicistat | N | PK | Cmax | AUC | Cmin
Dabigatran etexilate | 150 mg | 800/150 mg single dose | 14 | ↑ | 2.64 (2.29–3.05) | 2.64 (2.32–3.00) | -
 |  | 800/150 mg q.d. [800/150 mg q.d. for 14 days before co-administered with dabigatran etexilate.] | 14 | ↑ | 1.99 (1.72–2.30) | 1.88 (1.65–2.13) | -
N = number of subjects with data
q.d. = once daily

12.4 Microbiology

Mechanism of Action

Darunavir: Darunavir is an inhibitor of the HIV-1 protease. It selectively inhibits the cleavage of HIV-1 encoded Gag-Pol polyproteins in infected cells, thereby preventing the formation of mature virus particles.

Cobicistat: Cobicistat is a selective, mechanism-based inhibitor of CYPP450 of the CYP3A subfamily. Inhibition of CYP3A-mediated metabolism by cobicistat enhances the systemic exposure of CYP3A substrates.

Emtricitabine: Emtricitabine, a synthetic nucleoside analog of cytidine, is phosphorylated by cellular enzymes to form emtricitabine 5'-triphosphate. Emtricitabine 5'-triphosphate inhibits the activity of the HIV-1 reverse transcriptase (RT) by competing with the natural substrate deoxycytidine 5'-triphosphate and by being incorporated into nascent viral DNA, which results in chain termination. Emtricitabine 5'-triphosphate is a weak inhibitor of mammalian DNA polymerases α, β, ε, and mitochondrial DNA polymerase γ.

Tenofovir alafenamide: TAF is a phosphonamidate prodrug of tenofovir (2'-deoxyadenosine monophosphate analog). Plasma exposure to TAF allows for permeation into cells and then TAF is intracellularly converted to tenofovir through hydrolysis by cathepsin A. Tenofovir is subsequently phosphorylated by cellular kinases to the active metabolite tenofovir diphosphate. Tenofovir diphosphate inhibits HIV-1 replication through incorporation into viral DNA by the HIV RT, which results in DNA chain-termination. Tenofovir diphosphate is a weak inhibitor of mammalian DNA polymerases that include mitochondrial DNA polymerase γ and there is no evidence of toxicity to mitochondria in cell culture.

Antiviral Activity

Darunavir: Darunavir exhibits activity against laboratory strains and clinical isolates of HIV-1 and laboratory strains of HIV-2 in acutely infected T-cell lines, human PBMCs, and human monocytes/macrophages with median EC50values ranging from 1.2 to 8.5 nM (0.7 to 5.0 ng/mL). Darunavir demonstrates antiviral activity in cell culture against a broad panel of HIV-1 group M (A, B, C, D, E, F, G) and group O primary isolates with EC50values ranging from less than 0.1 to 4.3 nM. The EC50value of darunavir increases by a median factor of 5.4 in the presence of human serum.

Cobicistat: Cobicistat has no detectable antiviral activity in cell culture against HIV-1.

Emtricitabine: The antiviral activity of emtricitabine against laboratory and clinical isolates of HIV-1 was assessed in T lymphoblastoid cell lines, the MAGI-CCR5 cell line, and primary PBMCs. The EC50values for emtricitabine were in the range of 1.3–640 nM. Emtricitabine displayed antiviral activity in cell culture against HIV-1 clades A, B, C, D, E, F, and G (EC50values ranged from 7–75 nM) and showed strain specific activity against HIV-2 (EC50values ranged from 7–1,500 nM).

Tenofovir alafenamide: The antiviral activity of TAF against laboratory and clinical isolates of HIV-1 subtype B was assessed in lymphoblastoid cell lines, PBMCs, primary monocyte/macrophage cells, and CD4^+T lymphocytes. The EC50values for TAF ranged from 2.0 to 14.7 nM. TAF displayed antiviral activity in cell culture against all HIV-1 groups (M, N, O), including sub-types A, B, C, D, E, F, and G (EC50values ranged from 0.10 to 12.0 nM) and strain specific activity against HIV-2 (EC50values ranged from 0.91 to 2.63 nM).

The combination of darunavir, emtricitabine, and tenofovir alafenamide was not antagonistic in cell culture combination antiviral activity assays. In addition, darunavir, emtricitabine, and tenofovir alafenamide were not antagonistic with a panel of representative agents from the major classes of approved HIV antivirals (PIs, NRTIs, NNRTIs, and INSTIs). The antiviral activity of approved HIV antivirals was not antagonized by cobicistat.

Resistance

Cell Culture

Darunavir: In cell culture, HIV-1 isolates with a decreased susceptibility to darunavir have been selected and obtained from subjects treated with darunavir co-administered with ritonavir. Darunavir-resistant virus derived in cell culture from wild-type HIV-1 had 21- to 88-fold decreased susceptibility to darunavir and developed 2 to 4 of the following amino acid substitutions S37D, R41E/T, K55Q, H69Q, K70E, T74S, V77I, or I85V in the protease. Selection in cell culture of darunavir-resistant HIV-1 from nine HIV-1 strains harboring multiple PI resistance-associated substitutions resulted in the overall emergence of 22 mutations in the protease gene, coding for amino acid substitutions L10F, V11I, I13V, I15V, G16E, L23I, V32I, L33F, S37N, M46I, I47V, I50V, F53L, L63P, A71V, G73S, L76V, V82I, I84V, T91A/S, and Q92R, of which L10F, V32I, L33F, S37N, M46I, I47V, I50V, L63P, A71V, and I84V were the most prevalent. These darunavir-resistant viruses had at least eight protease substitutions and exhibited 50- to 641-fold decreases in darunavir susceptibility with final EC50values ranging from 125 nM to 3461 nM.

Emtricitabine: HIV-1 isolates with reduced susceptibility to emtricitabine were selected in cell culture and in subjects treated with emtricitabine. Reduced susceptibility to emtricitabine was associated with M184V or I substitutions in HIV-1 RT.

Tenofovir alafenamide: HIV-1 isolates with reduced susceptibility to TAF were selected in cell culture. HIV-1 isolates selected by TAF expressed a K65R substitution in HIV-1 RT, sometimes in the presence of S68N or L429I substitutions. In addition, a K70E substitution in HIV-1 RT was observed.

Clinical Trials

Darunavir resistance-associated substitutions (V11I, V32I, L33F, I47V, I50V, I54L or M, T74P, L76V, I84V, and L89V) in HIV-1 protease were derived from clinical trial data of antiretroviral therapy experienced patients, which were all protease inhibitor-experienced patients. Baseline International AIDS Society-USA (IAS-USA)-defined PI resistance substitutions confer reduced virologic response to darunavir.

In the AMBER clinical trial of subjects with no prior antiretroviral treatment history, there were 7 subjects with protocol-defined virologic failure and with HIV-1 RNA ≥400 copies/mL at failure or later timepoints who had post-baseline resistance data in the SYMTUZA arm. None of the subjects had detectable emergent darunavir resistance-associated substitutions or other primary protease inhibitor resistance-associated substitutions and only one subject had emergent M184M/I/V, which confers resistance to emtricitabine and lamivudine. In the comparative PREZCOBIX + emtricitabine/tenofovir disoproxil fumarate arm, there were 2 protocol-defined virologic failures with post-baseline resistance data and neither had detectable resistance emergence.

In the EMERALD clinical trial of virologically-suppressed subjects who switched to SYMTUZA, 1 subject who rebounded and 2 subjects who discontinued early from the study had post-baseline resistance genotypes. None of the subjects had darunavir, primary protease inhibitor, emtricitabine, or tenofovir resistance-associated substitutions. In the control arm, there were 3 subjects who rebounded with post-baseline genotypes and no resistance-associated substitutions were observed.

Cross-Resistance

Darunavir: Cross-resistance among PIs has been observed. Darunavir has a less than 10-fold decreased susceptibility in cell culture against 90% of 3309 clinical isolates resistant to amprenavir, atazanavir, indinavir, lopinavir, nelfinavir, ritonavir, saquinavir, and/or tipranavir showing that viruses resistant to these PIs remain susceptible to darunavir. A less than 10-fold decreased susceptibility was observed for the other PIs in 26% to 96% of these PI resistant clinical isolates [nelfinavir (26%), ritonavir (34%), lopinavir (46%), indinavir (57%), atazanavir (59%), saquinavir (64%), amprenavir (70%), and tipranavir (96%)].

Cross-resistance between darunavir and nucleoside/nucleotide reverse transcriptase inhibitors, non-nucleoside reverse transcriptase inhibitors, gp41 fusion inhibitors, CCR5 co-receptor antagonists, or integrase strand transfer inhibitors is unlikely because the viral targets are different.

Emtricitabine: Emtricitabine-resistant viruses with the M184V or I substitution were cross-resistant to lamivudine, but retained sensitivity to didanosine, stavudine, tenofovir, and zidovudine.

Tenofovir Alafenamide: Tenofovir resistance-associated substitutions K65R and K70E result in reduced susceptibility to abacavir, didanosine, emtricitabine, lamivudine, and tenofovir. HIV-1 with multiple thymidine analog substitutions (M41L, D67N, K70R, L210W, T215F/Y, K219Q/E/N/R) or multinucleoside resistant HIV-1 with a T69S double insertion mutation or with a Q151M substitution complex including K65R, showed reduced susceptibility to TAF in cell culture.

13. NONCLINICAL TOXICOLOGY

13.1 Carcinogenesis, Mutagenesis, Impairment of Fertility

Darunavir: Darunavir was evaluated for carcinogenic potential by oral gavage administration to mice and rats up to 104 weeks. Daily doses of 150, 450, and 1000 mg/kg were administered to mice and doses of 50, 150, and 500 mg/kg were administered to rats. A dose-related increase in the incidence of hepatocellular adenomas and carcinomas was observed in males and females of both species and an increase in thyroid follicular cell adenomas was observed in male rats. The observed hepatocellular findings in rodents are considered to be of limited relevance to humans. Repeated administration of darunavir to rats caused hepatic microsomal enzyme induction and increased thyroid hormone elimination, which predispose rats but not humans to thyroid neoplasms. At the highest tested doses, the systemic exposures to darunavir (based on AUC) were between 0.5- and 0.6-fold (mice) and was 0.9-fold (rats) of exposures observed in humans at the recommended therapeutic dose of darunavir in SYMTUZA. Darunavir was not mutagenic or genotoxic in a battery of in vitroand in vivoassays including bacterial reverse mutation (Ames), chromosomal aberration in human lymphocytes, and in vivomicronucleus test in mice.

Cobicistat: In a long-term carcinogenicity study in mice, no drug-related increases in tumor incidence were observed at doses up to 50 and 100 mg/kg/day in males and females, respectively. Cobicistat exposures at these doses were approximately 8.6 (male) and 20 (females) times, respectively, the human systemic exposure at the therapeutic daily dose of cobicistat in SYMTUZA. In a long-term carcinogenicity study of cobicistat in rats, an increased incidence of follicular cell adenomas and/or carcinomas in the thyroid gland was observed at doses of 25 and 50 mg/kg/day in males, and at 30 mg/kg/day in females. The follicular cell findings are considered to be rat-specific, secondary to hepatic microsomal enzyme induction and thyroid hormone imbalance, and are not relevant for humans. At the highest doses tested in the rat carcinogenicity study, systemic exposures were approximately 2 times the human systemic exposure at the therapeutic daily dose of cobicistat in SYMTUZA. Cobicistat was not genotoxic in the reverse mutation bacterial test (Ames test), mouse lymphoma, or rat micronucleus assays.

Emtricitabine: In long-term carcinogenicity studies of emtricitabine, no drug-related increases in tumor incidence were found in mice at doses up to 750 mg per kg per day (26 times the human systemic exposure at the recommended dose of emtricitabine in SYMTUZA) or in rats at doses up to 600 mg per kg per day (31 times the human systemic exposure at the recommended dose). Emtricitabine was not genotoxic in the reverse mutation bacterial test (Ames test), mouse lymphoma, or mouse micronucleus assays. Emtricitabine did not affect fertility in male rats at approximately 107 times or in male and female mice at approximately 88 times higher exposures (AUC) than in humans given the recommended 200 mg daily dose in SYMTUZA. Fertility was normal in the offspring of mice exposed daily from before birth (in utero) through sexual maturity at daily exposures (AUC) of approximately 88 times higher than human exposures at the recommended 200 mg daily dose.

Tenofovir alafenamide: Since TAF is rapidly converted to tenofovir and a lower tenofovir exposure in rats and mice was observed after TAF administration compared to TDF administration, carcinogenicity studies were conducted only with TDF. Long-term oral carcinogenicity studies of TDF in mice and rats were carried out at exposures up to approximately 10 times (mice) and 4 times (rats) those observed in humans at the 300 mg therapeutic dose of TDF for HIV-1 infection. The tenofovir exposure in these studies was approximately 167 times (mice) and 55 times (rat) those observed in humans after administration of the daily recommended dose of TAF. At the high dose in female mice, liver adenomas were increased at tenofovir exposures approximately 10 times (300 mg TDF) and 167 times (10 mg TAF) the exposure observed in humans. In rats, the study was negative for carcinogenic findings.

TAF was not genotoxic in the reverse mutation bacterial test (Ames test), mouse lymphoma, or rat micronucleus assays. There were no effects on fertility, mating performance, or early embryonic development when TAF was administered to male rats at a dose equivalent to 155 times the human dose based on body surface area comparisons for 28 days prior to mating and to female rats for 14 days prior to mating through Day 7 of gestation.

13.2 Animal Toxicology and/or Pharmacology

Minimal to slight infiltration of mononuclear cells in the posterior uvea was observed in dogs with similar severity after 3 and 9 month administration of tenofovir alafenamide; reversibility was seen after a 3-month recovery period. No eye toxicity was observed in the dog at systemic exposures of 3.5 (TAF) and 0.62 (tenofovir) times the exposure seen in humans with the recommended daily dose of TAF in SYMTUZA.

14. CLINICAL STUDIES

14.1 Clinical Trial Results in Subjects with HIV-1 Infection with no Prior Antiretroviral Treatment History

The efficacy of SYMTUZA in HIV-1 subjects with no prior antiretroviral treatment history was evaluated in the Phase 3 trial TMC114FD2HTX3001 [NCT02431247, (AMBER)] in which subjects were randomized in a 1:1 ratio to receive either SYMTUZA (N=362) or a combination of PREZCOBIX and FTC/TDF (N=363) once daily. The median age was 34.0 years (range 18–71), 88.3% were male, 83% White, 11% Black, and 2% Asian. The mean baseline plasma HIV-1 RNA was 4.5 log10copies/mL (range 1.3–6.7), and 18% had a baseline viral load ≥100,000 copies/mL. The median baseline CD4+ cell count was 453 cells/mm^3(range 38 to 1456 cells/mm^3).

Virologic outcomes at 48 weeks of treatment are presented in Table 11.

Table 11: Virologic Outcomes in AMBER at Week 48 in HIV-1 Subjects with No Prior Antiretroviral Treatment History
 | SYMTUZA N=362 | PREZCOBIX + FTC/TDF N=363
Virologic Response
HIV-1 RNA <50 copies/mL | 91% | 88%
Treatment difference [Based on stratum adjusted MH test where stratification factors are HIV-1 RNA level (≤100,000 or > 100,000 copies/mL) and CD4+ cell count (< 200 or ≥200 cells/µL).] | 2.7 (95% CI: -1.6; 7.1)
Virologic Failure [Included subjects who had ≥50 copies/mL in the Week 48 window; subjects who discontinued early due to lack or loss of efficacy; subjects who discontinued for reasons other than an adverse event (AE), death, or lack or loss of efficacy and at the time of discontinuation had a viral value of ≥ 50 copies/mL.] | 4% | 3%
No virologic data at Week 48 window [Day 295 – Day 378] | 4% | 8%
Reasons
Discontinued trial due to adverse event or death | 2% | 4%
Discontinued trial for other reasons [Other includes reasons such as withdrew consent, loss to follow-up, and non-compliance.] | 1% | 3%
Missing data during window but on trial | 1% | 1%

The mean increase from baseline in CD4+ cell count at Week 48 was 189 and 174 cells/mm^3in the SYMTUZA and PREZCOBIX + FTC/TDF groups, respectively.

14.2 Clinical Trial Results in Virologically-Suppressed Subjects with HIV-1 Infection Who Switched to SYMTUZA

Phase 3 trial TMC114IFD3013 [NCT02269917, (EMERALD)] evaluated the efficacy of SYMTUZA in virologically-suppressed (HIV-1 RNA less than 50 copies/mL) subjects with HIV-1 infection. Subjects were virologically suppressed for at least 2 months and no more than once had a viral load elevation above 50 HIV-1 RNA copies/mL during the year prior to enrollment. Subjects were on a stable antiretroviral regimen (for at least 6 months), consisting of a bPI [either darunavir once daily or atazanavir (both boosted with ritonavir or cobicistat), or lopinavir with ritonavir] combined with emtricitabine and TDF. Subjects had no history of failure on darunavir treatment and no known or suspected darunavir resistance-associated substitutions. Emtricitabine or tenofovir resistance-associated substitutions were not specifically excluded by the protocol. They either switched to SYMTUZA (N=763) or continued their treatment regimen (N=378) (randomized 2:1). Subjects had a median age of 46 years (range 19–78), 82% were male, 75% White, 21% Black, and 2% Asian. The median baseline CD4+ cell count was 628 cells/mm^3(range 111–1921 cells/mm^3). Overall, 15% (N=169) of subjects had prior virologic failure. Five subjects had archived tenofovir resistance-associated substitutions and 53 subjects had archived emtricitabine resistance-associated substitutions, mainly at RT position M184. All of these subjects with emtricitabine resistance-associated substitutions had HIV-1 RNA<50 copies/mL at Week 48 (N=50) or at the last on-treatment viral load (N=3). Virologic outcomes are presented in Table 12. Prior virologic failure did not impact treatment outcomes.

Table 12: Virologic Outcomes in EMERALD at Week 48 in HIV-1 Virologically-Suppressed Subjects Who Switched to SYMTUZA
 | SYMTUZA N=763 | bPI+FTC/TDF N=378
Virologic Failure [Included subjects who had ≥50 copies/mL in the Week 48 window; subjects who discontinued early due to lack or loss of efficacy; subjects who discontinued for reasons other than an adverse event (AE), death, or lack or loss of efficacy and at the time of discontinuation had a viral value ≥ 50 copies/mL.] | 1% | 1%
Treatment difference [Based on MH test adjusting for bPI at screening (ATV with rtv or COBI, DRV with rtv or COBI, LPV with rtv).] | 0.3 (95% CI: -0.7; 1.2)
HIV-1 RNA <50 copies/mL | 95% | 94%
No virologic data at Week 48 window [Day 295 – Day 378] | 4% | 6%
Reasons
Discontinued trial due to adverse event or death | 1% | 1%
Discontinued trial for other reasons [Other includes reasons such as withdrew consent, loss to follow-up, and non-compliance] | 3% | 4%
Missing data during window but on trial | <1% | 1%

The mean increase from baseline in CD4+ cell count at Week 48 was 20 cells/mm^3in subjects who switched to SYMTUZA and 8 cells/mm^3in subjects who stayed on their baseline PI + FTC/TDF.

14.3 Clinical Trial Results in Pediatric Subjects with HIV-1 Infection

The pharmacokinetic profile, safety, and antiviral activity of the components of SYMTUZA were evaluated in open-label clinical trials in pediatric subjects with HIV-1 infection aged 12 to less than 18 years: GS-US-216-0128 (N=7) and GS-US-292-0106 (N=50).

In the Phase 2/3 trial GS-US-216-0128, darunavir 800 mg and cobicistat 150 mg once daily with 2 NRTIs were evaluated in 7 virologically suppressed pediatric subjects aged 12 to less than 18 years and weighing at least 40 kg. Subjects had a median (range) age of 14 (12–16) years and a median (range) weight of 57 (45–78) kg. At baseline, plasma HIV-1 RNA was <50 copies/mL in all subjects, and the median (range) CD4+ cell count was 1,117 (658–2,416) cells/mm^3. At Week 48, the proportion of subjects who maintained HIV-1 RNA <50 copies/mL was 86%, and the median change in CD4+ cell count from baseline was -342 cells/mm^3(range -1,389 to 210 cells/mm^3). All 6 subjects with available data had CD4+ cell counts above 800 cells/mm^3at Week 48.

In the Phase 2/3 trial GS-US-292-0106, cobicistat 150 mg, emtricitabine 200 mg, and tenofovir alafenamide 10 mg, as part of a fixed-dose combination regimen together with elvitegravir 150 mg, were evaluated in 50 treatment-naïve pediatric subjects with HIV-1 aged 12 to less than 18 years and weighing at least 35 kg. Subjects had a median (range) age of 15 (12–17) years. At baseline, median (range) plasma HIV-1 RNA was 4.7 (3.3–6.5) log10copies/mL, median (range) CD4+ cell count was 456 (95–1,110) cells/mm^3, and 22% had baseline plasma HIV-1 RNA >100,000 copies/mL). At Week 48, the proportion of subjects who had HIV-1 RNA <50 copies/mL was 92%, and the median increase in CD4+ cell count from baseline was 220 cells/mm^3.

The use of SYMTUZA in pediatric patients weighing less than 40 kg has not been established [see Use in Specific Populations (8.4)].

16. HOW SUPPLIED/STORAGE AND HANDLING

SYMTUZA®(darunavir, cobicistat, emtricitabine, and tenofovir alafenamide) tablets are supplied as yellow to yellowish-brown, capsule-shaped, film-coated tablets debossed with "8121" on one side and "JG" on the other side.

SYMTUZA is packaged in bottles of 30 tablets (NDC 59676-800-30), with a silica gel desiccant and child-resistant closure.

Storage

- Store at 20°C–25°C (between 68°F–77°F); with excursions permitted to 15°C–30°C (59°F–86°F).
- Dispense only in the original container. Keep container tightly closed with desiccant inside to protect from moisture.
- Keep SYMTUZA out of reach of children.

17. PATIENT COUNSELING INFORMATION

Advise the patient to read the FDA-approved patient labeling (Patient Information).

Instructions for Use

Advise patients to take SYMTUZA with food every day on a regular dosing schedule, as missed doses can result in development of resistance. Inform patients not to alter the dose of SYMTUZA or discontinue therapy with SYMTUZA without consulting their physician. For patients who are unable to swallow tablets whole, SYMTUZA may be split using a tablet-cutter, and the entire dose should be consumed immediately after splitting [see Dosage and Administration (2.2)] .

Post-treatment Acute Exacerbation of Hepatitis B in Patients with HBV Co-Infection

Severe acute exacerbations of hepatitis B have been reported in patients who are coinfected with HBV and HIV-1 and have discontinued products containing emtricitabine and/or TDF, and may likewise occur with discontinuation of SYMTUZA [see Warnings and Precautions (5.1)] . Advise the patient to not discontinue SYMTUZA without first informing their healthcare provider.

Hepatotoxicity

Inform patients that drug-induced hepatitis (e.g., acute hepatitis, cytolytic hepatitis) and liver injury, including some fatalities, could potentially occur with SYMTUZA. Advise patients to contact their healthcare provider immediately if signs and symptoms of liver problems develop [see Warnings and Precautions (5.2)] .

Severe Skin Reactions

Inform patients that skin reactions ranging from mild to severe, including Stevens-Johnson syndrome, drug rash with eosinophilia and systemic symptoms, and toxic epidermal necrolysis, could potentially occur with SYMTUZA. Advise patients to contact their healthcare provider immediately if signs or symptoms of severe skin reactions develop, including but not limited to severe rash or rash accompanied with fever, general malaise, fatigue, muscle or joint aches, blisters, oral lesions, and/or conjunctivitis [see Warnings and Precautions (5.3)] .

Pregnancy

Advise patients that SYMTUZA is not recommended during pregnancy and to alert their healthcare provider if they get pregnant while taking SYMTUZA. Inform patients that there is an antiretroviral pregnancy registry to monitor fetal outcomes of pregnant individuals exposed to SYMTUZA [see Use in Specific Populations (8.1)] .

Lactation

Instruct individuals with HIV-1 infection not to breastfeed because HIV-1 can be passed to the baby in breast milk [see Use in Specific Populations (8.2)] .

Drug Interactions

SYMTUZA may interact with many drugs; therefore, inform patients of the potential serious drug interactions with SYMTUZA, and that some drugs are contraindicated with SYMTUZA and other drugs may require dosage adjustment. Advise patients to report to their healthcare provider the use of any other prescription or nonprescription medication or herbal products, including St. John's wort [see Contraindications (4), Warnings and Precautions (5.4), and Drug Interactions (7)] .

Immune Reconstitution Syndrome

Advise patients to inform their healthcare provider immediately of any symptoms of infection, as in some patients with advanced HIV infection (AIDS), signs and symptoms of inflammation from previous infections may occur soon after anti-HIV treatment is started [see Warnings and Precautions (5.5)] .

Renal Impairment

Advise patients to avoid taking SYMTUZA with concurrent or recent use of nephrotoxic agents. Renal impairment, including cases of acute renal failure, has been reported in association with the use of tenofovir prodrugs [see Warnings and Precautions (5.6)] .

Lactic Acidosis and Severe Hepatomegaly

Lactic acidosis and severe hepatomegaly with steatosis, including fatal cases, have been reported with use of drugs similar to SYMTUZA. Advise patients that they should stop SYMTUZA if they develop clinical symptoms suggestive of lactic acidosis or pronounced hepatotoxicity [see Warnings and Precautions (5.8)] .

Fat Redistribution

Inform patients that redistribution or accumulation of body fat may occur in patients receiving antiretroviral therapy, including SYMTUZA, and that the cause and long-term health effects of these conditions are not known at this time [see Warnings and Precautions (5.10)] .

Manufactured for:
Janssen Products, LP, Horsham PA 19044, USA

© 2018, 2020 Janssen Pharmaceutical Companies

PATIENT INFORMATION
SYMTUZA®(sim toó zah)
(darunavir, cobicistat, emtricitabine, and tenofovir alafenamide)
tablets

What is the most important information I should know about SYMTUZA?
SYMTUZA can cause serious side effects, including:

- Worsening of Hepatitis B virus infection (HBV).Your healthcare provider will test you for HBV before starting treatment with SYMTUZA. If you have HBV infection and take SYMTUZA, your HBV may get worse (flare-up) if you stop taking SYMTUZA. A "flare-up" is when your HBV infection suddenly returns in a worse way than before.
  - Do not stop taking SYMTUZA without first talking to your healthcare provider.
  - Do not run out of SYMTUZA. Refill your prescription or talk to your healthcare provider before your SYMTUZA is all gone.
  - If you stop taking SYMTUZA, your healthcare provider will need to check your health often and do blood tests regularly for several months to check your HBV infection, or give you a medicine to treat your HBV infection. Tell your healthcare provider about any new or unusual symptoms you may have after you stop taking SYMTUZA.
- Change in liver enzymes. People with a history of hepatitis B or C virus infection or who have certain liver enzyme changes may have an increased risk of developing new or worsening liver problems during treatment with SYMTUZA. Liver problems can also happen during treatment with SYMTUZA in people without a history of liver disease. Your healthcare provider may need to do tests to check your liver enzymes before and during treatment with SYMTUZA.
- Severe liver problems.In rare cases, severe liver problems can happen that can lead to death. Tell your healthcare provider right away if you get these symptoms:skin or the white part of your eyes turns yellow, dark "tea-colored" urine, light-colored stools, loss of appetite for several days or longer, nausea, vomiting, or stomach-area pain.

SYMTUZA may cause severe or life-threatening skin reactions or rash. Sometimes these skin reactions and skin rashes can become severe and require treatment in a hospital. Call your healthcare provider right away if you develop a rash. Stop taking SYMTUZAand call your healthcare provider right away if you develop any skin changes with symptoms below:

- fever
- tiredness
- muscle or joint pain

- blisters or skin lesions
- mouth sores or ulcers
- red or inflamed eyes, like "pink eye" (conjunctivitis)

See " What are the possible side effects of SYMTUZA?" for more information about side effects.

What is SYMTUZA?
SYMTUZA is a prescription medicine that is used without other antiretroviral medicines to treat Human Immunodeficiency Virus-1 (HIV-1) infection in adults and in children who weigh at least 88 pounds (40 kg) who:

- have not received anti-HIV-1 medicines in the past, or
- when their healthcare provider determines that they meet certain requirements.

HIV-1 is the virus that causes Acquired Immune Deficiency Syndrome (AIDS).
SYMTUZA contains the prescription medicines darunavir, cobicistat, emtricitabine, and tenofovir alafenamide.
It is not known if SYMTUZA is safe and effective in children weighing less than 88 pounds (40 kg).

Who should not take SYMTUZA?
Do not take SYMTUZA with any of the following medicines:

- alfuzosin
- carbamazepine
- colchicine, if you have liver or kidney problems
- dronedarone
- elbasvir and grazoprevir
- ergot-containing medicines, such as:
  - dihydroergotamine
  - ergotamine tartrate
  - methylergonovine
- ivabradine
- lomitapide
- lovastatin or a product that contains lovastatin
- lurasidone
- midazolam, when taken by mouth
- naloxegol
- phenobarbital
- phenytoin
- pimozide
- ranolazine
- rifampin
- sildenafil, when used for the treatment of pulmonary arterial hypertension (PAH)
- simvastatin or a product that contains simvastatin
- St. John's wort (Hypericum perforatum), or a product that contains St. John's wort
- triazolam

Serious problems can happen if you take any of these medicines with SYMTUZA. This is not a complete list of medicines. Therefore, tell your healthcare provider about all medicines you take.

Before taking SYMTUZA, tell your healthcare provider about all of your medical conditions, including if you:

- have liver problems, including hepatitis B or hepatitis C
- have kidney problems
- are allergic to sulfa (sulfonamide)
- have diabetes
- have hemophilia
- are pregnant or plan to become pregnant.
  - It is not known if SYMTUZA will harm your unborn baby.
  - SYMTUZA should not be used during pregnancy because you may not have enough SYMTUZA in your body during pregnancy.
  - Tell your healthcare provider if you become pregnant while taking SYMTUZA. Your healthcare provider will prescribe different medicines if you become pregnant while taking SYMTUZA.
    Pregnancy Registry: There is a pregnancy registry for those who take antiretroviral medicines during pregnancy. The purpose of the registry is to collect information about the health of you and your baby. Talk to your healthcare provider about how you can take part in this registry.
- are breastfeeding or plan to breastfeed. Do not breastfeed if you take SYMTUZA.
  - You should not breastfeed if you have HIV-1 because of the risk of passing HIV to your baby.
  - One of the medicines in SYMTUZA called emtricitabine can pass into your breast milk. It is not known if the other medicines in SYMTUZA can pass into your breast milk.
  - Talk to your healthcare provider about the best way to feed your baby.

Tell your healthcare provider about all the medicines you take, including prescription and over-the-counter medicines, topical creams, vitamins, and herbal supplements. Some medicines interact with SYMTUZA. Keep a list of your medicines to show your healthcare provider and pharmacist.

- You can ask your healthcare provider or pharmacist for a list of medicines that interact with SYMTUZA.
- Do not start taking a new medicine without telling your healthcare provider.Your healthcare provider can tell you if it is safe to take SYMTUZA with other medicines.

How should I take SYMTUZA?

- Take SYMTUZA exactly as your healthcare provider tells you.
- Do not change your dose or stop taking SYMTUZA without talking to your healthcare provider.
- Take SYMTUZA 1 time a day with food.
- If you have difficulty swallowing, the tablet may be split using a tablet-cutter. After splitting the tablet, the entire dose (both halves) should then be taken right away.
- Do not miss a dose of SYMTUZA.
- When your SYMTUZA supply starts to run low, get more from your healthcare provider or pharmacy. This is very important because the amount of virus in your blood may increase if the medicine is stopped for even a short time. The virus may develop resistance to SYMTUZA and become harder to treat.
- If you take too much SYMTUZA, call your healthcare provider or go to the nearest hospital emergency room right away.

What are the possible side effects of SYMTUZA?
SYMTUZA may cause serious side effects, including:

- See " What is the most important information I should know about SYMTUZA?"
- Changes in your immune system (Immune Reconstitution Syndrome)can happen when you start taking HIV-1 medicines. Your immune system may get stronger and begin to fight infections that have been hidden in your body for a long time. Tell your healthcare provider right away if you start having new symptoms after starting your HIV-1 medicine.
- New or worse kidney problems, including kidney failure.Your healthcare provider should do blood and urine tests to check your kidneys before you start and while you are taking SYMTUZA. Your healthcare provider may tell you to stop taking SYMTUZA if you develop new or worse kidney problems.
- Too much lactic acid in your blood (lactic acidosis).Too much lactic acid is a serious but rare medical emergency that can lead to death. Tell your healthcare provider right away if you get these symptoms:weakness or being more tired than usual, unusual muscle pain, being short of breath or fast breathing, stomach pain with nausea and vomiting, cold or blue hands and feet, feel dizzy or lightheaded, or a fast or abnormal heartbeat.
- Diabetes and high blood sugar (hyperglycemia).Some people who take protease inhibitors including SYMTUZA can get high blood sugar, develop diabetes, or your diabetes can get worse. Tell your healthcare provider if you notice an increase in thirst or if you start urinating more often while taking SYMTUZA.
- Changes in body fatcan happen in people who take HIV-1 medicines. The changes may include an increased amount of fat in the upper back and neck ("buffalo hump"), breast, and around the middle of your body (trunk). Loss of fat from the legs, arms, and face may also happen. The exact cause and long-term health effects of these conditions are not known.
- Increased bleeding for hemophiliacs.Some people with hemophilia have increased bleeding with protease inhibitors.

The most common side effects of SYMTUZA, include:

- diarrhea
- rash
- nausea
- fatigue

- headache
- stomach problems
- gas

These are not all of the possible side effects of SYMTUZA.
Call your doctor for medical advice about side effects. You may report side effects to FDA at 1-800-FDA-1088.

How should I store SYMTUZA?

- Store SYMTUZA tablets at room temperature between 68°F to 77°F (20°C to 25°C).
- The SYMTUZA bottle contains a desiccant and has a child-resistant cap.
- Keep the SYMTUZA container tightly closed with the desiccant inside of it to protect SYMTUZA from moisture.

Keep SYMTUZA out of reach of children.

General information about the safe and effective use of SYMTUZA.
Medicines are sometimes prescribed for purposes other than those listed in a Patient Information leaflet. Do not use SYMTUZA for a condition for which it was not prescribed. Do not give SYMTUZA to other people, even if they have the same symptoms that you have. It may harm them.
You can ask your healthcare provider or pharmacist for information about SYMTUZA that is written for health professionals.

What are the ingredients in SYMTUZA?
Active ingredient : darunavir, cobicistat, emtricitabine, and tenofovir alafenamide
Inactive ingredients: colloidal silicon dioxide, croscarmellose sodium, magnesium stearate, and microcrystalline cellulose. The tablets are film-coated with a coating material containing polyethylene glycol (macrogol), polyvinyl alcohol (partially hydrolyzed), talc, titanium dioxide, and yellow ferric oxide.
Manufactured for: Janssen Products, LP, Horsham PA 19044, USA
© 2018, 2020 Janssen Pharmaceutical Companies
For more information call 1-800-526-7736.

This Patient Information has been approved by the U.S. Food and Drug Administration.

Revised: 03/2023

PRINCIPAL DISPLAY PANEL - 30 Tablet Bottle Label

NDC 59676-800-30

Symtuza™
(darunavir, cobicistat,
emtricitabine, and tenofovir
alafenamide) tablets

800 mg / 150 mg /
200 mg / 10 mg

Each tablet contains darunavir
ethanolate equivalent to 800 mg
of darunavir, 150 mg of cobicistat,
200 mg of emtricitabine, and
tenofovir alafenamide fumarate
equivalent to 10 mg of tenofovir
alafenamide.

Rx only
30 Tablets